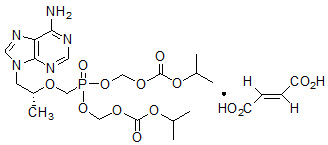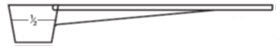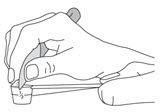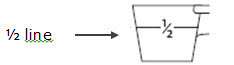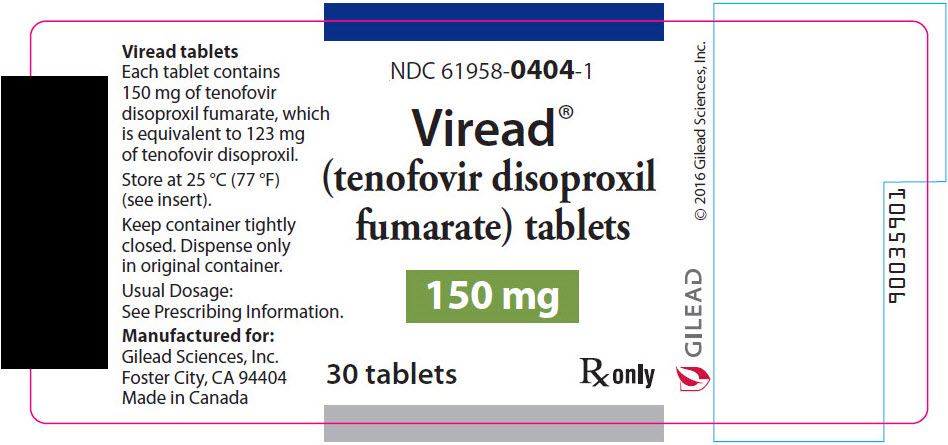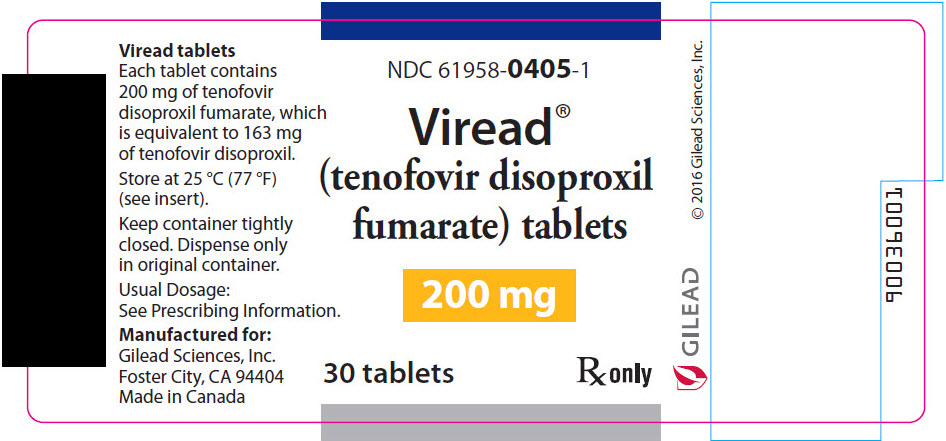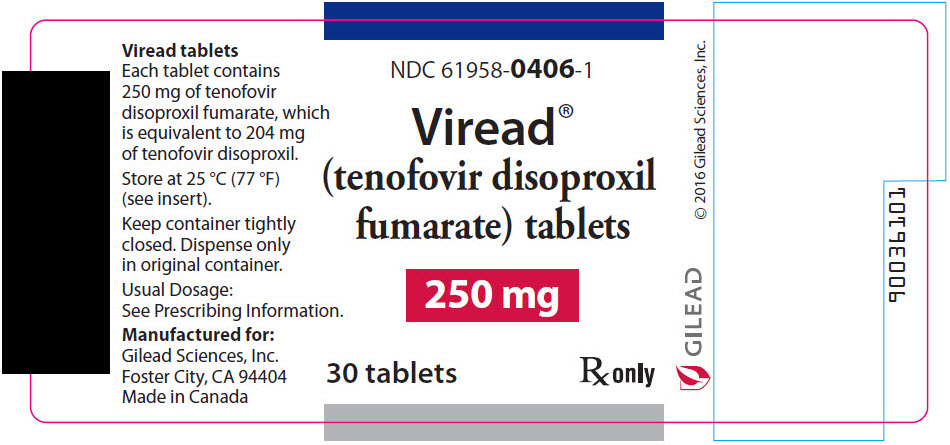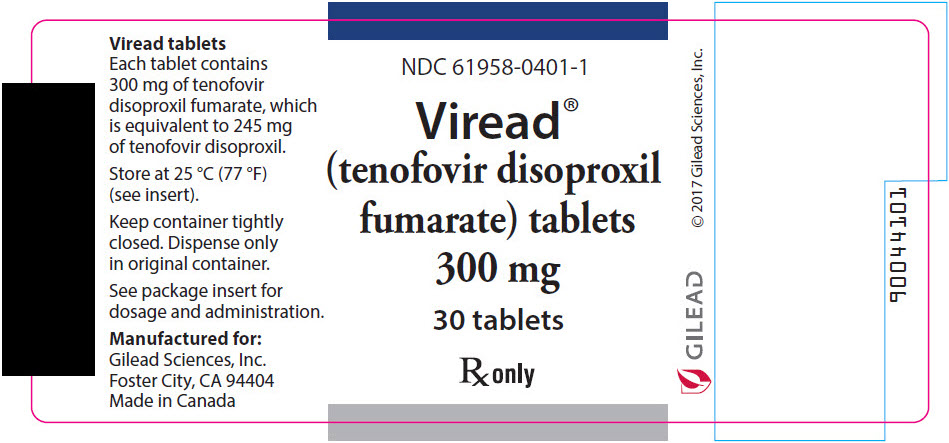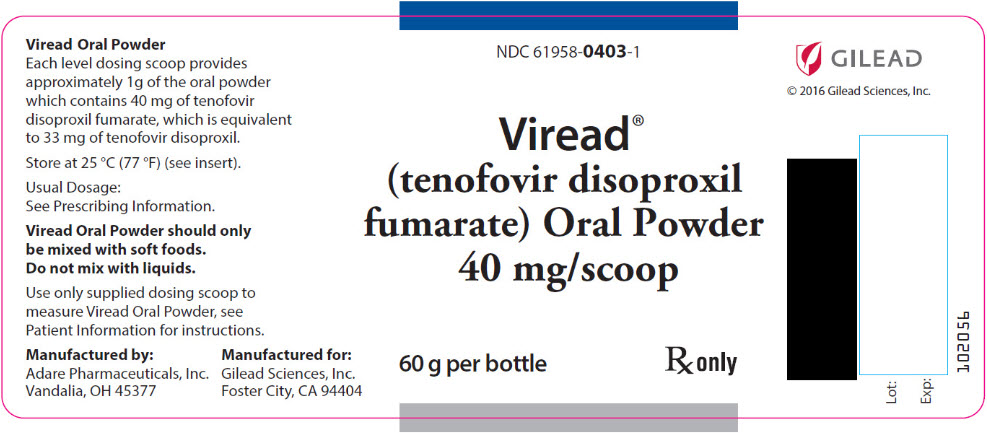 DRUG LABEL: Viread
NDC: 61958-0404 | Form: TABLET, COATED
Manufacturer: Gilead Sciences, Inc.
Category: prescription | Type: HUMAN PRESCRIPTION DRUG LABEL
Date: 20250218

ACTIVE INGREDIENTS: TENOFOVIR DISOPROXIL FUMARATE 150 mg/1 1
INACTIVE INGREDIENTS: STARCH, CORN; CROSCARMELLOSE SODIUM; LACTOSE MONOHYDRATE; MICROCRYSTALLINE CELLULOSE; MAGNESIUM STEARATE; TITANIUM DIOXIDE; TRIACETIN; HYPROMELLOSE 2910 (15000 MPA.S)

HIGHLIGHTS OF PRESCRIBING INFORMATION

These highlights do not include all the information needed to use VIREAD safely and effectively. See full prescribing information for VIREAD.
VIREAD® (tenofovir disoproxil fumarate) tablets, for oral use
VIREAD® (tenofovir disoproxil fumarate) powder, for oral use
Initial U.S. Approval: 2001

WARNING: POSTTREATMENT ACUTE EXACERBATION OF HEPATITIS B

See full prescribing information for complete boxed warning.

Severe acute exacerbations of hepatitis B virus (HBV) have been reported in HBV-infected patients who have discontinued anti-hepatitis B therapy, including VIREAD. Hepatic function should be monitored closely in HBV-infected patients who discontinue VIREAD. If appropriate, resumption of anti-hepatitis B therapy may be warranted. (5.1)

RECENT MAJOR CHANGES

Indications and Usage, Chronic Hepatitis B (1.2) | 12/2018
Dosage and Administration (2.1, 2.2, 2.3, 2.4) | 12/2018
Warnings and Precautions (5.1, 5.2, 5.5, 5.7) | 12/2018
Early Virologic Failure | Removed 12/2018

1 INDICATIONS AND USAGE

VIREAD is a nucleotide analog HIV-1 reverse transcriptase inhibitor and an HBV reverse transcriptase inhibitor and is indicated:

- in combination with other antiretroviral agents for the treatment of HIV-1 infection in adults and pediatric patients 2 years of age and older weighing at least 10 kg. (1.1)
- for the treatment of chronic hepatitis B in adults and pediatric patients 2 years and older weighing at least 10 kg. (1.2)

2 DOSAGE AND ADMINISTRATION

- Testing: Prior to or when initiating VIREAD test for hepatitis B virus infection and HIV-1 infection. Prior to initiation and during use of VIREAD, on a clinically appropriate schedule, assess serum creatinine, estimated creatinine clearance, urine glucose, and urine protein in all patients. In patients with chronic kidney disease, also assess serum phosphorous. (2.1)
- Recommended tablet dosage in adults and pediatric patients weighing at least 35 kg: One VIREAD 300 mg tablet once daily taken orally without regard to food. (2.2)
- Recommended dosage in pediatric patients at least 2 years of age and adults:
  - Tablets: For patients weighing at least 17 kg who can swallow an intact tablet, one VIREAD tablet (150 mg, 200 mg, 250 mg, or 300 mg based on body weight) once daily taken orally without regard to food. (2.2)
  - Oral powder: For patients weighing at least 10 kg and unable to swallow a tablet, 8 mg per kg VIREAD oral powder (up to a maximum of 300 mg) taken once daily with food. (2.3)
- Recommended dosage in renally impaired adult patients:
  - Creatinine clearance (CrCl) 30–49 mL/min: 300 mg every 48 hours. (2.4)
  - CrCl 10–29 mL/min: 300 mg every 72 to 96 hours. (2.4)
  - Hemodialysis: 300 mg every 7 days or after approximately 12 hours of dialysis. (2.4)

3 DOSAGE FORMS AND STRENGTHS

- Tablets: 150 mg, 200 mg, 250 mg, and 300 mg of tenofovir disoproxil fumarate. (3)
- Oral Powder: 40 mg per 1 g of oral powder of tenofovir disoproxil fumarate. (3)

4 CONTRAINDICATIONS

None. (4)

5 WARNINGS AND PRECAUTIONS

- New onset or worsening renal impairment: Can include acute renal failure and Fanconi syndrome. Avoid administering VIREAD with concurrent or recent use of nephrotoxic drugs. (5.2)
- HIV testing: HIV antibody testing should be offered to all HBV-infected patients before initiating therapy with VIREAD. VIREAD should only be used as part of an appropriate antiretroviral combination regimen in HIV-infected patients with or without HBV coinfection. (5.3)
- Immune reconstitution syndrome: May necessitate further evaluation and treatment. (5.4)
- Decreases in bone mineral density (BMD): Consider assessment of BMD in patients with a history of pathologic fracture or other risk factors for osteoporosis or bone loss. (5.5)
- Lactic acidosis/severe hepatomegaly with steatosis: Discontinue treatment in patients who develop symptoms or laboratory findings suggestive of lactic acidosis or pronounced hepatotoxicity. (5.6)

6 ADVERSE REACTIONS

- In HIV-infected adult subjects: Most common adverse reactions (incidence greater than or equal to 10%, Grades 2–4) were rash, diarrhea, nausea, headache, pain, depression, and asthenia. (6.1)
- In HBV-infected subjects with compensated liver disease: Most common adverse reaction (all grades) was nausea (9%). (6.1)
- In HBV-infected subjects with decompensated liver disease: Most common adverse reactions (incidence greater than or equal to 10%, all grades) were abdominal pain, nausea, insomnia, pruritus, vomiting, dizziness, and pyrexia. (6.1)
- In pediatric subjects: Adverse reactions in pediatric subjects were consistent with those observed in adults. (6.1)

To report SUSPECTED ADVERSE REACTIONS, contact Gilead Sciences, Inc. at 1-800-GILEAD-5 or FDA at 1-800-FDA-1088 or www.fda.gov/medwatch

7 DRUG INTERACTIONS

- Tenofovir disoproxil fumarate increases didanosine concentrations. Dose reduction and close monitoring for didanosine toxicity are warranted. (7.2)
- Coadministration decreases atazanavir concentrations. When coadministered with VIREAD, use atazanavir given with ritonavir. (7.2)
- Coadministration of VIREAD with certain HIV-1 protease inhibitors or certain drugs to treat HCV increases tenofovir concentrations. Monitor for evidence of tenofovir toxicity. (7.2)
- Consult Full Prescribing Information prior to and during treatment for important drug interactions. (7.2)

8 USE IN SPECIFIC POPULATIONS

Lactation: Breastfeeding in HIV-1 infected mothers is not recommended due to the potential for HIV-1 transmission. (8.2)

FULL PRESCRIBING INFORMATION

WARNING: POSTTREATMENT ACUTE EXACERBATION OF HEPATITIS B

Severe acute exacerbations of hepatitis B virus (HBV) have been reported in HBV-infected patients who have discontinued anti-hepatitis B therapy, including VIREAD. Hepatic function should be monitored closely with both clinical and laboratory follow-up for at least several months in HBV-infected patients who discontinue anti-hepatitis B therapy, including VIREAD. If appropriate, resumption of anti-hepatitis B therapy may be warranted [see Warnings and Precautions (5.1)].

1 INDICATIONS AND USAGE

1.1 HIV-1 Infection

VIREAD is indicated in combination with other antiretroviral agents for the treatment of human immunodeficiency virus type 1 (HIV-1) infection in adults and pediatric patients 2 years of age and older weighing at least 10 kg.

1.2 Chronic Hepatitis B

VIREAD is indicated for the treatment of chronic hepatitis B virus (HBV) in adults and pediatric patients 2 years of age and older weighing at least 10 kg.

2 DOSAGE AND ADMINISTRATION

2.1 Testing Prior to Initiation of VIREAD for Treatment of HIV-1 Infection or Chronic Hepatitis B

Prior to or when initiating VIREAD, test patients for HBV infection and HIV-1 infection. VIREAD alone should not be used in patients with HIV-1 infection [see Warnings and Precautions (5.3)].

Prior to initiation and during use of VIREAD, on a clinically appropriate schedule, assess serum creatinine, estimated creatinine clearance, urine glucose and urine protein in all patients. In patients with chronic kidney disease, also assess serum phosphorus [see Warnings and Precautions (5.2)].

2.2 Recommended Tablet Dosage in Adults and Pediatric Patients 2 Years and Older Weighing at Least 17 kg

The recommended dosage of VIREAD in adults and pediatric patients weighing at least 35 kg is one 300 mg tablet taken orally once daily without regard to food. The dosage for VIREAD is the same for both HIV and HBV indications.

The recommended dosage of VIREAD tablet in adults and pediatric patients 2 years and older weighing at least 17 kg is 8 mg of tenofovir disoproxil fumarate (TDF) per kg of body weight (up to a maximum of 300 mg) once daily. Dosage for pediatric patients 2 years and older weighing between 17 kg and 35 kg and able to swallow an intact tablet is provided in Table 1. Weight should be monitored periodically and the VIREAD dose adjusted accordingly.

Table 1 Recommended Dosing for Patients 2 Years and Older and Weighing at Least 17 kg Using VIREAD Tablets
Body Weight (kg) | Dosing of VIREAD Tablets
17 to less than 22 | one 150 mg tablet once daily
22 to less than 28 | one 200 mg tablet once daily
28 to less than 35 | one 250 mg tablet once daily
at least 35 | one 300 mg tablet once daily

2.3 Recommended Oral Powder Dosage in Adults and Pediatric Patients 2 Years and Older Weighing at Least 10 kg

The recommended dosage of VIREAD oral powder in adults and pediatric patients 2 years and older weighing at least 10 kg who are unable to swallow a tablet is 8 mg of TDF per kg of body weight (up to a maximum of 300 mg) once daily administered as oral powder (see Table 2). Weight should be monitored periodically and the VIREAD dose adjusted accordingly.

VIREAD oral powder should be measured only with the supplied dosing scoop. One level scoop delivers 1 g of powder, which contains 40 mg of TDF. VIREAD oral powder should be mixed in a container with 2 to 4 ounces of soft food not requiring chewing (e.g., applesauce, baby food, yogurt). The entire mixture should be ingested immediately to avoid a bitter taste. Do not administer VIREAD oral powder in a liquid as the powder may float on top of the liquid even after stirring. Further patient instructions on how to administer VIREAD oral powder with the supplied dosing scoop are provided in the FDA-approved patient labeling (Patient Information).

Table 2 Dosing for Patients 2 Years and Older Weighing at least 10 kg Using VIREAD Oral Powder
Body Weight (kg) | Dosing of VIREAD Oral Powder | Total Daily Dosage (40 mg per scoop)
10 to less than 12 | 2 scoops once daily | 80 mg
12 to less than 14 | 2.5 scoops once daily | 100 mg
14 to less than 17 | 3 scoops once daily | 120 mg
17 to less than 19 | 3.5 scoops once daily | 140 mg
19 to less than 22 | 4 scoops once daily | 160 mg
22 to less than 24 | 4.5 scoops once daily | 180 mg
24 to less than 27 | 5 scoops once daily | 200 mg
27 to less than 29 | 5.5 scoops once daily | 220 mg
29 to less than 32 | 6 scoops once daily | 240 mg
32 to less than 34 | 6.5 scoops once daily | 260 mg
34 to less than 35 | 7 scoops once daily | 280 mg
at least 35 | 7.5 scoops once daily | 300 mg

2.4 Dosage Adjustment in Patients with Renal Impairment

Significant increase in drug exposures occurred when VIREAD was administered to subjects with moderate to severe renal impairment (creatinine clearance below 50 mL/min). Table 3 provides dosage interval adjustment for patients with renal impairment. No dosage adjustment of VIREAD tablets 300 mg is necessary for patients with mild renal impairment (creatinine clearance 50–80 mL/min) [see Warnings and Precautions (5.3), Use in Specific Populations (8.6), and Clinical Pharmacology (12.3)].

Table 3 Dosage Interval Adjustment for Adult Patients with Altered Creatinine Clearance
 | Creatinine Clearance (mL/min) [Calculated using ideal (lean) body weight.] |  |  | Hemodialysis Patients
 | 50 or greater | 30–49 | 10–29 | Hemodialysis Patients
Recommended 300 mg Dosing Interval | Every 24 hours | Every 48 hours | Every 72 to 96 hours | Every 7 days or after a total of approximately 12 hours of dialysis [Generally once weekly assuming 3 hemodialysis sessions a week of approximately 4 hours' duration. VIREAD should be administered following completion of dialysis.]

No data are available to make dosage recommendations in patients with creatinine clearance below 10 mL/min who are not on hemodialysis.

No data are available to make dosage recommendations in pediatric patients with renal impairment.

3 DOSAGE FORMS AND STRENGTHS

VIREAD is available as tablets in four dose strengths or as an oral powder.

- 150 mg Tablets: 150 mg of tenofovir disoproxil fumarate (TDF) (equivalent to 123 mg of tenofovir disoproxil): triangle shaped, white, film coated, debossed with "GSI" on one side and with "150" on the other side.
- 200 mg Tablets: 200 mg of TDF (equivalent to 163 mg of tenofovir disoproxil): round shaped, white, film coated, debossed with "GSI" on one side and with "200" on the other side.
- 250 mg Tablets: 250 mg of TDF (equivalent to 204 mg of tenofovir disoproxil): capsule shaped, white, film coated, debossed with "GSI" on one side and with "250" on the other side.
- 300 mg Tablets: 300 mg of TDF (equivalent to 245 mg of tenofovir disoproxil): almond shaped, light blue, film coated, debossed with "GILEAD" and "4331" on one side and with "300" on the other side.
- Oral Powder: white, taste-masked, coated granules containing 40 mg of TDF (equivalent to 33 mg of tenofovir disoproxil) per level scoop. Each level scoop contains 1 gram of oral powder.

4 CONTRAINDICATIONS

None.

5 WARNINGS AND PRECAUTIONS

5.1 Severe Acute Exacerbation of Hepatitis B in Patients with HBV Infection

All patients should be tested for the presence of chronic hepatitis B virus (HBV) before or when initiating VIREAD [see Dosage and Administration (2.1)].

Discontinuation of anti-HBV therapy, including VIREAD, may be associated with severe acute exacerbations of hepatitis B. Patients infected with HBV who discontinue VIREAD should be closely monitored with both clinical and laboratory follow-up for at least several months after stopping treatment. If appropriate, resumption of anti-hepatitis B therapy may be warranted, especially in patients with advanced liver disease or cirrhosis, since posttreatment exacerbation of hepatitis may lead to hepatic decompensation and liver failure.

5.2 New Onset or Worsening Renal Impairment

Tenofovir is principally eliminated by the kidney. Renal impairment, including cases of acute renal failure and Fanconi syndrome (renal tubular injury with severe hypophosphatemia), has been reported with the use of VIREAD [see Adverse Reactions (6.2)].

Prior to initiation and during use of VIREAD, on a clinically appropriate schedule, assess serum creatinine, estimated creatinine clearance, urine glucose, and urine protein in all patients. In patients with chronic kidney disease, also assess serum phosphorus.

Dosing interval adjustment of VIREAD and close monitoring of renal function are recommended in all patients with creatinine clearance below 50 mL/min [see Dosage and Administration (2.4)]. No safety or efficacy data are available in patients with renal impairment who received VIREAD using these dosing guidelines, so the potential benefit of VIREAD therapy should be assessed against the potential risk of renal toxicity.

VIREAD should be avoided with concurrent or recent use of a nephrotoxic agent (e.g., high-dose or multiple non-steroidal anti-inflammatory drugs [NSAIDs]) [see Drug Interactions (7.1)]. Cases of acute renal failure after initiation of high-dose or multiple NSAIDs have been reported in HIV-infected patients with risk factors for renal dysfunction who appeared stable on TDF. Some patients required hospitalization and renal replacement therapy. Alternatives to NSAIDs should be considered, if needed, in patients at risk for renal dysfunction.

Persistent or worsening bone pain, pain in extremities, fractures and/or muscular pain or weakness may be manifestations of proximal renal tubulopathy and should prompt an evaluation of renal function in patients at risk of renal dysfunction.

5.3 Patients Coinfected with HIV-1 and HBV

Due to the risk of development of HIV-1 resistance, VIREAD should only be used in HIV-1 and HBV coinfected patients as part of an appropriate antiretroviral combination regimen.

HIV-1 antibody testing should be offered to all HBV-infected patients before initiating therapy with VIREAD. It is also recommended that all patients with HIV-1 be tested for the presence of chronic hepatitis B before initiating treatment with VIREAD.

5.4 Immune Reconstitution Syndrome

Immune reconstitution syndrome has been reported in HIV-1 infected patients treated with combination antiretroviral therapy, including VIREAD. During the initial phase of combination antiretroviral treatment, HIV-1 infected patients whose immune system responds may develop an inflammatory response to indolent or residual opportunistic infections (such as Mycobacterium avium infection, cytomegalovirus, Pneumocystis jirovecii pneumonia [PCP], or tuberculosis), which may necessitate further evaluation and treatment.

Autoimmune disorders (such as Graves' disease, polymyositis, and Guillain-Barré syndrome) have also been reported to occur in the setting of immune reconstitution; however, the time to onset is more variable, and can occur many months after initiation of treatment.

5.5 Bone Loss and Mineralization Defects

Bone Mineral Density

In clinical trials in HIV-1 infected adults, VIREAD was associated with slightly greater decreases in bone mineral density (BMD) and increases in biochemical markers of bone metabolism, suggesting increased bone turnover relative to comparators [see Adverse Reactions (6.1)]. Serum parathyroid hormone levels and 1,25 Vitamin D levels were also higher in subjects receiving VIREAD.

Clinical trials evaluating VIREAD in pediatric subjects were conducted. Under normal circumstances, BMD increases rapidly in pediatric patients. In HIV-1 infected subjects 2 years to less than 18 years of age, bone effects were similar to those observed in adult subjects and suggest increased bone turnover. Total body BMD gain was less in the VIREAD-treated HIV-1 infected pediatric subjects as compared to the control groups. Similar trends were observed in chronic HBV-infected pediatric subjects 2 years to less than 18 years of age. In all pediatric trials, normal skeletal growth (height) was not affected for the duration of the clinical trials [see Adverse Reactions (6.1)].

The effects of VIREAD-associated changes in BMD and biochemical markers on long-term bone health and future fracture risk in adults and pediatric subjects 2 years and older are unknown. The long-term effect of lower spine and total body BMD on skeletal growth in pediatric patients, and in particular, the effects of long-duration exposure in younger children is unknown.

Although the effect of supplementation with calcium and vitamin D was not studied, such supplementation may be beneficial. Assessment of BMD should be considered for adult and pediatric patients who have a history of pathologic bone fracture or other risk factors for osteoporosis or bone loss. If bone abnormalities are suspected, appropriate consultation should be obtained.

Mineralization Defects

Cases of osteomalacia associated with proximal renal tubulopathy, manifested as bone pain or pain in extremities and which may contribute to fractures, have been reported in association with VIREAD use [see Adverse Reactions (6.2)]. Arthralgia and muscle pain or weakness have also been reported in cases of proximal renal tubulopathy. Hypophosphatemia and osteomalacia secondary to proximal renal tubulopathy should be considered in patients at risk of renal dysfunction who present with persistent or worsening bone or muscle symptoms while receiving TDF-containing products [see Warnings and Precautions (5.2)].

5.6 Lactic Acidosis/Severe Hepatomegaly with Steatosis

Lactic acidosis and severe hepatomegaly with steatosis, including fatal cases, have been reported with the use of nucleoside analogs, including TDF, alone or in combination with other antiretrovirals. Treatment with VIREAD should be suspended in any patient who develops clinical or laboratory findings suggestive of lactic acidosis or pronounced hepatotoxicity (which may include hepatomegaly and steatosis even in the absence of marked transaminase elevations).

5.7 Risk of Adverse Reactions Due to Drug Interactions

The concomitant use of VIREAD and other drugs may result in known or potentially significant drug interactions, some of which may lead to possible clinically significant adverse reactions from greater exposures of concomitant drugs [see Drug Interactions (7.2)].

See Table 12 for steps to prevent or manage these possible and known significant drug interactions, including dosing recommendations. Consider the potential for drug interactions prior to and during therapy with VIREAD; review concomitant medications during therapy with VIREAD; and monitor for adverse reactions associated with the concomitant drugs.

6 ADVERSE REACTIONS

The following adverse reactions are discussed in other sections of the labeling:

- Severe Acute Exacerbation of Hepatitis B in Patients with HBV Infection [see Warnings and Precautions (5.1)].
- New Onset or Worsening Renal Impairment [see Warnings and Precautions (5.2)].
- Immune Reconstitution Syndrome [see Warnings and Precautions (5.4)].
- Bone Loss and Mineralization Defects [see Warnings and Precautions (5.5)].
- Lactic Acidosis/Severe Hepatomegaly with Steatosis [see Warnings and Precautions (5.6)].

6.1 Clinical Trials Experience

Because clinical trials are conducted under widely varying conditions, adverse reaction rates observed in the clinical trials of a drug cannot be directly compared to rates in the clinical trials of another drug and may not reflect the rates observed in practice.

Adverse Reactions from Clinical Trials Experience in HIV-1 Infected Adults

More than 12,000 subjects have been treated with VIREAD alone or in combination with other antiretroviral medicinal products for periods of 28 days to 215 weeks in clinical trials and expanded access programs. A total of 1,544 subjects have received VIREAD 300 mg once daily in clinical trials; over 11,000 subjects have received VIREAD in expanded access programs.

The most common adverse reactions (incidence greater than or equal to 10%, Grades 2–4) identified from any of the 3 large controlled clinical trials include rash, diarrhea, headache, pain, depression, asthenia, and nausea.

Clinical Trials in Treatment-Naïve HIV-1 Infected Adult Subjects

In Trial 903, 600 antiretroviral-naïve subjects received VIREAD (N=299) or stavudine (d4T) (N=301) administered in combination with lamivudine (3TC) and efavirenz (EFV) for 144 weeks. The most common adverse reactions were mild to moderate gastrointestinal events and dizziness. Mild adverse reactions (Grade 1) were common with a similar incidence in both arms and included dizziness, diarrhea, and nausea. Table 4 provides the treatment-emergent adverse reactions (Grades 2–4) occurring in greater than or equal to 5% of subjects treated in any treatment group.

Table 4 Selected Adverse Reactions [Frequencies of adverse reactions are based on all treatment-emergent adverse events, regardless of relationship to study drug.] (Grades 2–4) Reported in ≥5% in Any Treatment Group in Trial 903 (0–144 Weeks)
 | VIREAD+3TC+EFV | d4T+3TC+EFV
 | N=299 | N=301
Rash event [Rash event includes rash, pruritus, maculopapular rash, urticaria, vesiculobullous rash, and pustular rash.] | 18% | 12%
Headache | 14% | 17%
Pain | 13% | 12%
Diarrhea | 11% | 13%
Depression | 11% | 10%
Back pain | 9% | 8%
Nausea | 8% | 9%
Fever | 8% | 7%
Abdominal pain | 7% | 12%
Asthenia | 6% | 7%
Anxiety | 6% | 6%
Vomiting | 5% | 9%
Insomnia | 5% | 8%
Arthralgia | 5% | 7%
Pneumonia | 5% | 5%
Dyspepsia | 4% | 5%
Dizziness | 3% | 6%
Myalgia | 3% | 5%
Lipodystrophy [Lipodystrophy represents a variety of investigator-described adverse events not a protocol-defined syndrome.] | 1% | 8%
Peripheral neuropathy [Peripheral neuropathy includes peripheral neuritis and neuropathy.] | 1% | 5%

Laboratory Abnormalities: Table 5 provides a list of laboratory abnormalities (Grades 3–4) observed in Trial 903. With the exception of fasting cholesterol and fasting triglyceride elevations that were more common in the d4T group (40% and 9%) compared with the VIREAD group (19% and 1%), respectively, laboratory abnormalities observed in this trial occurred with similar frequency in the VIREAD and d4T treatment arms.

Table 5 Grades 3–4 Laboratory Abnormalities Reported in ≥1% of VIREAD-Treated Subjects in Trial 903 (0–144 Weeks)
 | VIREAD+3TC+EFV | d4T+3TC+EFV
 | N=299 | N=301
Any ≥ Grade 3 Laboratory Abnormality | 36% | 42%
Fasting Cholesterol (>240 mg/dL) | 19% | 40%
Creatine Kinase (M: >990 U/L; F: >845 U/L) | 12% | 12%
Serum Amylase (>175 U/L) | 9% | 8%
AST (M: >180 U/L; F: >170 U/L) | 5% | 7%
ALT (M: >215 U/L; F: >170 U/L) | 4% | 5%
Hematuria (>100 RBC/HPF) | 7% | 7%
Neutrophils (<750/mm^3) | 3% | 1%
Fasting Triglycerides (>750 mg/dL) | 1% | 9%

Changes in Bone Mineral Density: In HIV-1 infected adult subjects in Trial 903, there was a significantly greater mean percentage decrease from baseline in BMD at the lumbar spine in subjects receiving VIREAD + 3TC + EFV (−2.2% ± 3.9) compared with subjects receiving d4T + 3TC + EFV (−1.0% ± 4.6) through 144 weeks. Changes in BMD at the hip were similar between the two treatment groups (−2.8% ± 3.5 in the VIREAD group vs. −2.4% ± 4.5 in the d4T group). In both groups, the majority of the reduction in BMD occurred in the first 24–48 weeks of the trial and this reduction was sustained through Week 144. Twenty-eight percent of VIREAD-treated subjects vs. 21% of d4T-treated subjects lost at least 5% of BMD at the spine or 7% of BMD at the hip. Clinically relevant fractures (excluding fingers and toes) were reported in 4 subjects in the VIREAD group and 6 subjects in the d4T group. In addition, there were significant increases in biochemical markers of bone metabolism (serum bone-specific alkaline phosphatase, serum osteocalcin, serum C telopeptide, and urinary N telopeptide) and higher serum parathyroid hormone levels and 1,25 Vitamin D levels in the VIREAD group relative to the d4T group; however, except for bone-specific alkaline phosphatase, these changes resulted in values that remained within the normal range [see Warnings and Precautions (5.5)].

In Trial 934, 511 antiretroviral-naïve subjects received efavirenz (EFV) administered in combination with either emtricitabine (FTC) + VIREAD (N=257) or zidovudine (AZT)/lamivudine (3TC) (N=254) for 144 weeks. The most common adverse reactions (incidence greater than or equal to 10%, all grades) included diarrhea, nausea, fatigue, headache, dizziness, depression, insomnia, abnormal dreams, and rash. Table 6 provides the treatment-emergent adverse reactions (Grades 2–4) occurring in greater than or equal to 5% of subjects treated in any treatment group.

Table 6 Selected Adverse Reactions [Frequencies of adverse reactions are based on all treatment-emergent adverse events, regardless of relationship to study drug.] (Grades 2–4) Reported in ≥5% in Any Treatment Group in Trial 934 (0–144 Weeks)
 | VIREAD [From Weeks 96 to 144 of the trial, subjects received TRUVADA® with EFV in place of VIREAD + FTC with EFV.] +FTC+EFV | AZT/3TC+EFV
 | N=257 | N=254
Fatigue | 9% | 8%
Depression | 9% | 7%
Nausea | 9% | 7%
Diarrhea | 9% | 5%
Dizziness | 8% | 7%
Upper respiratory tract infections | 8% | 5%
Sinusitis | 8% | 4%
Rash event [Rash event includes rash, exfoliative rash, rash generalized, rash macular, rash maculopapular, rash pruritic, and rash vesicular.] | 7% | 9%
Headache | 6% | 5%
Insomnia | 5% | 7%
Nasopharyngitis | 5% | 3%
Vomiting | 2% | 5%

Laboratory Abnormalities: Laboratory abnormalities observed in this trial were generally consistent with those seen in previous trials (Table 7).

Table 7 Significant Laboratory Abnormalities Reported in ≥1% of Subjects in Any Treatment Group in Trial 934 (0–144 Weeks)
 | VIREAD+FTC+EFV [From Weeks 96 to 144 of the trial, subjects received TRUVADA with EFV in place of VIREAD + FTC with EFV.] | AZT/3TC+EFV
 | N=257 | N=254
Any ≥ Grade 3 Laboratory Abnormality | 30% | 26%
Fasting Cholesterol (>240 mg/dL) | 22% | 24%
Creatine Kinase (M: >990 U/L; F: >845 U/L) | 9% | 7%
Serum Amylase (>175 U/L) | 8% | 4%
Alkaline Phosphatase (>550 U/L) | 1% | 0%
AST (M: >180 U/L; F: >170 U/L) | 3% | 3%
ALT (M: >215 U/L; F: >170 U/L) | 2% | 3%
Hemoglobin (<8.0 mg/dL) | 0% | 4%
Hyperglycemia (>250 mg/dL) | 2% | 1%
Hematuria (>75 RBC/HPF) | 3% | 2%
Glycosuria (≥3+) | <1% | 1%
Neutrophils (<750/mm^3) | 3% | 5%
Fasting Triglycerides (>750 mg/dL) | 4% | 2%

Clinical Trials in Treatment-Experienced HIV-1 Infected Adult Subjects

In Trial 907, the adverse reactions seen in HIV-1 infected treatment-experienced subjects were generally consistent with those seen in treatment-naïve subjects, including mild to moderate gastrointestinal events, such as nausea, diarrhea, vomiting, and flatulence. Less than 1% of subjects discontinued participation in the clinical trials due to gastrointestinal adverse reactions. Table 8 provides the treatment-emergent adverse reactions (Grades 2–4) occurring in greater than or equal to 3% of subjects treated in any treatment group.

Table 8 Selected Adverse Reactions [Frequencies of adverse reactions are based on all treatment-emergent adverse events, regardless of relationship to study drug.] (Grades 2–4) Reported in ≥3% in Any Treatment Group in Trial 907 (0–48 Weeks)
 | VIREAD N=368 (Week 0–24) | Placebo N=182 (Week 0–24) | VIREAD N=368 (Week 0–48) | Placebo Crossover to VIREAD N=170 (Week 24–48)
Body as a Whole
Asthenia | 7% | 6% | 11% | 1%
Pain | 7% | 7% | 12% | 4%
Headache | 5% | 5% | 8% | 2%
Abdominal pain | 4% | 3% | 7% | 6%
Back pain | 3% | 3% | 4% | 2%
Chest pain | 3% | 1% | 3% | 2%
Fever | 2% | 2% | 4% | 2%
Digestive System
Diarrhea | 11% | 10% | 16% | 11%
Nausea | 8% | 5% | 11% | 7%
Vomiting | 4% | 1% | 7% | 5%
Anorexia | 3% | 2% | 4% | 1%
Dyspepsia | 3% | 2% | 4% | 2%
Flatulence | 3% | 1% | 4% | 1%
Respiratory
Pneumonia | 2% | 0% | 3% | 2%
Nervous System
Depression | 4% | 3% | 8% | 4%
Insomnia | 3% | 2% | 4% | 4%
Peripheral neuropathy [Peripheral neuropathy includes peripheral neuritis and neuropathy.] | 3% | 3% | 5% | 2%
Dizziness | 1% | 3% | 3% | 1%
Skin and Appendage
Rash event [Rash event includes rash, pruritus, maculopapular rash, urticaria, vesiculobullous rash, and pustular rash.] | 5% | 4% | 7% | 1%
Sweating | 3% | 2% | 3% | 1%
Musculoskeletal
Myalgia | 3% | 3% | 4% | 1%
Metabolic
Weight loss | 2% | 1% | 4% | 2%

Laboratory Abnormalities: Table 9 provides a list of Grade 3–4 laboratory abnormalities observed in Trial 907. Laboratory abnormalities occurred with similar frequency in the VIREAD and placebo groups.

Table 9 Grades 3–4 Laboratory Abnormalities Reported in ≥1% of VIREAD-Treated Subjects in Trial 907 (0–48 Weeks)
 | VIREAD N=368 (Week 0–24) | Placebo N=182 (Week 0–24) | VIREAD N=368 (Week 0–48) | Placebo Crossover to VIREAD N=170 (Week 24–48)
Any ≥ Grade 3 Laboratory Abnormality | 25% | 38% | 35% | 34%
Triglycerides (>750 mg/dL) | 8% | 13% | 11% | 9%
Creatine Kinase (M: >990 U/L; F: >845 U/L) | 7% | 14% | 12% | 12%
Serum Amylase (>175 U/L) | 6% | 7% | 7% | 6%
Glycosuria (≥3+) | 3% | 3% | 3% | 2%
AST (M: >180 U/L; F: >170 U/L) | 3% | 3% | 4% | 5%
ALT (M: >215 U/L; F: >170 U/L) | 2% | 2% | 4% | 5%
Serum Glucose (>250 U/L) | 2% | 4% | 3% | 3%
Neutrophils (<750/mm^3) | 1% | 1% | 2% | 1%

Adverse Reactions from Clinical Trials Experience in HIV-1 Infected Pediatric Subjects 2 Years and Older

Assessment of adverse reactions is based on two randomized trials (Trials 352 and 321) in 184 HIV-1 infected pediatric subjects (2 years to less than 18 years of age) who received treatment with VIREAD (N=93) or placebo/active comparator (N=91) in combination with other antiretroviral agents for 48 weeks [see Clinical Studies (14.3)]. The adverse reactions observed in subjects who received treatment with VIREAD were consistent with those observed in clinical trials in adults.

In Trial 352, 89 pediatric subjects (2 years to less than 12 years of age) received VIREAD for a median exposure of 104 weeks. Of these, 4 subjects discontinued from the trial due to adverse reactions consistent with proximal renal tubulopathy. Three of these 4 subjects presented with hypophosphatemia and also had decreases in total body or spine BMD Z-score [see Warnings and Precautions (5.5)].

Changes in Bone Mineral Density: In Trial 321 (12 years to less than 18 years of age), the mean rate of BMD gain at Week 48 was less in the VIREAD group compared to the placebo group. Six VIREAD-treated subjects and one placebo-treated subject had significant (greater than 4%) lumbar spine BMD loss at Week 48. Changes from baseline BMD Z-scores were −0.341 for lumbar spine and −0.458 for total body in the 28 subjects who were treated with VIREAD for 96 weeks. In Trial 352 (2 years to less than 12 years of age), the mean rate of BMD gain in lumbar spine at Week 48 was similar between the VIREAD and the d4T or AZT treatment groups. Total body BMD gain was less in the VIREAD group compared to the d4T or AZT treatment group. One VIREAD-treated subject and none of the d4T- or AZT-treated subjects experienced significant (greater than 4%) lumbar spine BMD loss at Week 48. Changes from baseline in BMD Z-scores were −0.012 for lumbar spine and −0.338 for total body in the 64 subjects who were treated with VIREAD for 96 weeks. In both trials, skeletal growth (height) appeared to be unaffected for the duration of the clinical trials [see Warnings and Precautions (5.5)].

Adverse Reactions from Clinical Trials Experience in HBV-Infected Adults

Clinical Trials in Adult Subjects with Chronic Hepatitis B and Compensated Liver Disease

In controlled clinical trials in 641 subjects with chronic hepatitis B (0102 and 0103), more subjects treated with VIREAD during the 48-week double-blind period experienced nausea: 9% with VIREAD versus 2% with HEPSERA®. Other treatment-emergent adverse reactions reported in more than 5% of subjects treated with VIREAD included: abdominal pain, diarrhea, headache, dizziness, fatigue, nasopharyngitis, back pain, and skin rash.

In Trials 0102 and 0103, during the open-label phase of treatment with VIREAD (weeks 48–384), 2% of subjects (13/585) experienced a confirmed increase in serum creatinine of 0.5 mg/dL from baseline. No significant change in the tolerability profile was observed with continued treatment for up to 384 weeks.

Laboratory Abnormalities: Table 10 provides a list of Grade 3–4 laboratory abnormalities through Week 48. Grades 3–4 laboratory abnormalities were similar in subjects continuing VIREAD treatment for up to 384 weeks in these trials.

Table 10 Grades 3–4 Laboratory Abnormalities Reported in ≥1% of VIREAD-Treated Subjects in Trials 0102 and 0103 (0–48 Weeks)
 | VIREAD N=426 | HEPSERA N=215
Any ≥ Grade 3 Laboratory Abnormality | 19% | 13%
Creatine Kinase (M: >990 U/L; F: >845 U/L) | 2% | 3%
Serum Amylase (>175 U/L) | 4% | 1%
Glycosuria (≥3+) | 3% | <1%
AST (M: >180 U/L; F: >170 U/L) | 4% | 4%
ALT (M: >215 U/L; F: >170 U/L) | 10% | 6%

The overall incidence of on-treatment ALT flares (defined as serum ALT greater than 2 × baseline and greater than 10 × ULN, with or without associated symptoms) was similar between VIREAD (2.6%) and HEPSERA (2%). ALT flares generally occurred within the first 4 to 8 weeks of treatment and were accompanied by decreases in HBV DNA levels. No subject had evidence of decompensation. ALT flares typically resolved within 4 to 8 weeks without changes in study medication.

The adverse reactions observed in subjects with chronic hepatitis B and lamivudine resistance who received treatment with VIREAD were consistent with those observed in other HBV clinical trials in adults.

Clinical Trials in Adult Subjects with Chronic Hepatitis B and Decompensated Liver Disease

In Trial 0108, a small randomized, double-blind, active-controlled trial, subjects with chronic HBV and decompensated liver disease received treatment with VIREAD or other antiviral drugs for up to 48 weeks [see Clinical Studies (14.4)]. Among the 45 subjects receiving VIREAD, the most frequently reported treatment-emergent adverse reactions of any severity were abdominal pain (22%), nausea (20%), insomnia (18%), pruritus (16%), vomiting (13%), dizziness (13%), and pyrexia (11%). Two of 45 (4%) subjects died through Week 48 of the trial due to progression of liver disease. Three of 45 (7%) subjects discontinued treatment due to an adverse event. Four of 45 (9%) subjects experienced a confirmed increase in serum creatinine of 0.5 mg/dL (1 subject also had a confirmed serum phosphorus less than 2 mg/dL through Week 48). Three of these subjects (each of whom had a Child-Pugh score greater than or equal to 10 and MELD score greater than or equal to 14 at entry) developed renal failure. Because both VIREAD and decompensated liver disease may have an impact on renal function, the contribution of VIREAD to renal impairment in this population is difficult to ascertain.

One of 45 subjects experienced an on-treatment hepatic flare during the 48-week trial.

Adverse Reactions from Clinical Trials Experience in HBV-Infected Pediatric Subjects 2 Years and Older

Assessment of adverse reactions in pediatric subjects infected with chronic HBV is based on two randomized trials: Trial GS-US-174-0115 in 106 subjects (12 years to less than 18 years of age) receiving treatment with VIREAD (N=52) or placebo (N=54) for 72 weeks and Trial GS-US-174-0144 in 89 subjects (2 years to less than 12 years of age) receiving treatment with VIREAD (N=60) or placebo (N=29) for 48 weeks [see Clinical Studies (14.5)]. The adverse reactions observed in pediatric subjects who received treatment with VIREAD were consistent with those observed in clinical trials of VIREAD in adults.

In Trial 115 (12 years to less than 18 years of age) and Trial 144 (2 years to less than 12 years of age), both the VIREAD and placebo treatment arms experienced an overall increase in mean lumbar spine and total body BMD over 72 and 48 weeks, respectively, as expected for a pediatric population (Table 11). In Trial 115, the mean percentage BMD gains from baseline to Week 72 in lumbar spine and total body BMD in VIREAD-treated subjects were less than the mean percentage BMD gains observed in placebo-treated subjects (Table 11).Three subjects (6%) in the VIREAD group and two subjects (4%) in the placebo group had significant (greater than or equal to 4%) lumbar spine BMD loss at Week 72. In Trial 144 (2 years to less than 12 years of age), mean percentage BMD gains from baseline to Week 48 in lumbar spine and total body BMD in VIREAD-treated subjects were less than the mean percentage BMD gains observed in placebo-treated subjects. At Week 48, the cumulative percentage of subjects with greater than or equal to 4% decreases in spine or whole body BMD was numerically higher for subjects in the TDF group compared with the placebo group (Table 11). As observed in pediatric studies of HIV-infected subjects, normal skeletal growth (height) was not affected for the duration of the clinical trial [see Warnings and Precautions (5.5)].

Table 11 Change in Bone Mineral Density from Baseline in Pediatric Subjects 2 Years to <12 Years of Age (Trials 115 and 144)
 | Trial 115 (Week 72) |  | Trial 144 (Week 48)
 | VIREAD (N=52) | Placebo (N=54) | VIREAD (N=60) | Placebo (N=29)
Mean percentage change in BMD
Lumbar spine | +5% | +8% | +4% | +8%
Total body | +3% | +5% | +5% | +9%
Cumulative incidence of ≥4% decrease in BMD
Lumbar spine | 6% | 4% | 18% | 7%
Total body | 0% | 2% | 7% | 0%
Baseline BMD Z-score (mean)
Lumbar spine | −0.43 | −0.28 | +0.02 | −0.29
Total body | −0.20 | −0.26 | +0.11 | −0.05
Mean change in BMD Z-score
Lumbar spine | -0.05 | +0.07 | −0.12 | +0.14
Total body | -0.15 | +0.06 | −0.18 | +0.22

The effects of VIREAD-associated changes in BMD and biochemical markers on long-term bone health and future fracture risk in pediatric patients 2 years and older are unknown. The long-term effect of lower spine and total body BMD on skeletal growth in pediatric patients 2 years and older, and in particular, the effects of long-duration exposure in younger children is unknown [see Warnings and Precautions (5.5)].

6.2 Postmarketing Experience

The following adverse reactions have been identified during postapproval use of VIREAD. Because postmarketing reactions are reported voluntarily from a population of uncertain size, it is not always possible to reliably estimate their frequency or establish a causal relationship to drug exposure.

Immune System Disorders
allergic reaction, including angioedema

Metabolism and Nutrition Disorders
lactic acidosis, hypokalemia, hypophosphatemia

Respiratory, Thoracic, and Mediastinal Disorders
dyspnea

Gastrointestinal Disorders
pancreatitis, increased amylase, abdominal pain

Hepatobiliary Disorders
hepatic steatosis, hepatitis, increased liver enzymes (most commonly AST, ALT gamma GT)

Skin and Subcutaneous Tissue Disorders
rash

Musculoskeletal and Connective Tissue Disorders
rhabdomyolysis, osteomalacia (manifested as bone pain and which may contribute to fractures), muscular weakness, myopathy

Renal and Urinary Disorders
acute renal failure, renal failure, acute tubular necrosis, Fanconi syndrome, proximal renal tubulopathy, interstitial nephritis (including acute cases), nephrogenic diabetes insipidus, renal insufficiency, increased creatinine, proteinuria, polyuria

General Disorders and Administration Site Conditions
asthenia

The following adverse reactions, listed under the body system headings above, may occur as a consequence of proximal renal tubulopathy: rhabdomyolysis, osteomalacia, hypokalemia, muscular weakness, myopathy, hypophosphatemia.

7 DRUG INTERACTIONS

7.1 Drugs Affecting Renal Function

Tenofovir is primarily eliminated by the kidneys [see Clinical Pharmacology (12.3)]. Coadministration of VIREAD with drugs that are eliminated by active tubular secretion may increase concentrations of tenofovir and/or the coadministered drug. Some examples include, but are not limited to, acyclovir, cidofovir, ganciclovir, valacyclovir, valganciclovir, aminoglycosides (e.g., gentamicin), and high-dose or multiple NSAIDs [see Warnings and Precautions (5.2)]. Drugs that decrease renal function may increase concentrations of tenofovir.

In the treatment of chronic hepatitis B, VIREAD should not be administered in combination with HEPSERA (adefovir dipivoxil).

7.2 Established and Significant Interactions

Table 12 provides a listing of established or clinically significant drug interactions. The drug interactions described are based on studies conducted with TDF [see Clinical Pharmacology (12.3)].

Table 12 Established and Significant [This table is not all inclusive.] Drug Interactions: Alteration in Dose or Regimen May Be Recommended Based on Drug Interaction Trials
Concomitant Drug Class: Drug Name | Effect on Concentration [↑=Increase, ↓=Decrease] | Clinical Comment
NRTI: didanosine | ↑ didanosine | Patients receiving VIREAD and didanosine should be monitored closely for didanosine-associated adverse reactions. Discontinue didanosine in patients who develop didanosine-associated adverse reactions. Higher didanosine concentrations could potentiate didanosine-associated adverse reactions, including pancreatitis, and neuropathy. Suppression of CD4+ cell counts has been observed in patients receiving VIREAD with didanosine 400 mg daily. In patients weighing greater than 60 kg, reduce the didanosine dose to 250 mg when it is coadministered with VIREAD. In patients weighing less than 60 kg, reduce the didanosine dose to 200 mg when it is coadministered with VIREAD. When coadministered, VIREAD and Videx EC may be taken under fasted conditions or with a light meal (less than 400 kcal, 20% fat).
HIV-1 Protease Inhibitors: atazanavir | ↓ atazanavir | When coadministered with VIREAD, atazanavir 300 mg should be given with ritonavir 100 mg.
lopinavir/ritonavir atazanavir/ritonavir darunavir/ritonavir | ↑ tenofovir | Monitor patients receiving VIREAD concomitantly with lopinavir/ritonavir, ritonavir-boosted atazanavir, or ritonavir-boosted darunavir for TDF-associated adverse reactions. Discontinue VIREAD in patients who develop TDF-associated adverse reactions.
Hepatitis C Antiviral Agents: sofosbuvir/velpatasvir sofosbuvir/velpatasvir/voxilaprevir | ↑ tenofovir | Monitor patients receiving VIREAD concomitantly with EPCLUSA® (sofosbuvir/velpatasvir) for adverse reactions associated with TDF.
ledipasvir/sofosbuvir |  | Monitor patients receiving VIREAD concomitantly with HARVONI® (ledipasvir/sofosbuvir) without an HIV-1 protease inhibitor/ritonavir or an HIV-1 protease inhibitor/cobicistat combination, for adverse reactions associated with TDF. In patients receiving VIREAD concomitantly with HARVONI and an HIV-1 protease inhibitor/ritonavir or an HIV-1 protease inhibitor/cobicistat combination, consider an alternative HCV or antiretroviral therapy, as the safety of increased tenofovir concentrations in this setting has not been established. If coadministration is necessary, monitor for adverse reactions associated with TDF.

8 USE IN SPECIFIC POPULATIONS

8.1 Pregnancy

Pregnancy Exposure Registry

There is a pregnancy exposure registry that monitors pregnancy outcomes in women exposed to VIREAD during pregnancy. Healthcare providers are encouraged to register patients by calling the Antiretroviral Pregnancy Registry (APR) at 1-800-258-4263.

Risk Summary

Available data from the APR show no increase in the overall risk of major birth defects with first trimester exposure for tenofovir disoproxil fumarate (TDF) (2.1%) compared with the background rate for major birth defects of 2.7% in a U.S. reference population of the Metropolitan Atlanta Congenital Defects Program (MACDP) (see Data). The rate of miscarriage for individual drugs is not reported in the APR. In the U.S. general population, the estimated background risk of miscarriage in clinically recognized pregnancies is 15–20%.

Published studies in HBV-infected subjects do not report an increased risk of adverse pregnancy-related outcomes with the use of VIREAD during the third trimester of pregnancy (see Data).

In animal reproduction studies, no adverse developmental effects were observed when TDF was administered at doses/exposures ≥ 14 (TDF) and 2.7 (tenofovir) times those of the recommended daily dose of VIREAD (see Data).

Data

Human Data

Based on prospective reports from the APR exposures to TDF-containing regimens during pregnancy resulting in live births (including 3,342 exposed in the first trimester and 1,475 exposed in the second/third trimester), there was no increase in overall major birth defects with TDF compared with the background birth defect rate of 2.7% in a U.S. reference population of the MACDP. The prevalence of major birth defects in live births was 2.3% (95% CI: 1.8% to 2.8%) with first trimester exposure to TDF-containing regimens, and 2.1% (95% CI: 1.4% to 3.0%) with the second/third trimester exposure to TDF-containing regimens.

Prospective reports from the APR of overall major birth defects in pregnancies exposed to TDF are compared with a U.S. background major birth defect rate. Methodological limitations of the APR include the use of MACDP as the external comparator group. Limitations of using an external comparator include differences in methodology and populations, as well as confounding due to the underlying disease.

In published data from three controlled clinical trials, a total of 327 pregnant women with chronic HBV infection were administered VIREAD from 28 to 32 weeks gestation through 1 to 2 months postpartum and followed for up to 12 months after delivery. There were no new safety findings in pregnant women compared with the known safety profile of VIREAD in HBV-infected adults. An increased risk of adverse pregnancy-related outcomes was not observed; 2 stillbirths were identified, and there was 1 major birth defect (talipes) and 1 occurrence of multiple congenital abnormalities (not further specified) in VIREAD-exposed infants. Infants were followed for up to 12 months after delivery; there were no clinically relevant drug-related safety findings in infants exposed to VIREAD during late gestation.

Animal Data

TDF was administered orally to pregnant rats (at 0, 50, 150, or 450 mg/kg/day) and rabbits (at 0, 30, 100, or 300 mg/kg/day) through organogenesis (on gestation days 7 through 17, and 6 through 18, respectively). No significant toxicological effects were observed in embryo-fetal toxicity studies performed with TDF in rats at doses up to 14 times the human dose based on body surface area comparisons and in rabbits at doses up to 19 times the human dose based on body surface area comparisons. In a pre/postnatal development study in rats, TDF was administered orally through lactation at doses up to 600 mg/kg/day; no adverse effects were observed in the offspring at tenofovir exposures of approximately 2.7 times higher than human exposures at the recommended daily dose of VIREAD.

8.2 Lactation

Risk Summary

Based on published data, tenofovir has been shown to be present in human breast milk (see Data). It is not known if tenofovir affects milk production or has effects on the breastfed child.

Treatment of HIV-1 infection:

The Centers for Disease Control and Prevention recommend that HIV-1 infected mothers not breastfeed their infants to avoid risking postnatal transmission of HIV-1.

Because of the potential for: (1) HIV transmission (in HIV-negative infants); (2) developing viral resistance (in HIV-positive infants); and (3) adverse reactions in a breastfed infant similar to those seen in adults, instruct mothers not to breastfeed if they are taking VIREAD for the treatment of HIV-1.

Treatment of HBV infection:

The developmental and health benefits of breastfeeding should be considered along with the mother's clinical need for VIREAD and any potential adverse effects on the breastfed infant from VIREAD or from the underlying maternal condition.

Data

In a study of 50 HIV-uninfected, breastfeeding women on a tenofovir-containing regimen initiated between 1 and 24 weeks postpartum (median 13 weeks), tenofovir was undetectable in the plasma of most infants after 7 days of treatment in mothers. There were no serious adverse events in mothers or infants.

8.4 Pediatric Use

Pediatric Patients 2 Years and Older with HIV-1 Infection

The safety and effectiveness of VIREAD in pediatric patients 2 years to less than 18 years of age is supported by data from two randomized trials. Trial 352 was a randomized controlled trial in 92 HIV-1 treatment experienced subjects 2 years to less than 12 years of age who were virologically suppressed on a stavudine- or zidovudine-containing regimen and were randomized to either switch to a VIREAD-containing regimen (N=44) or stay on their original regimen (N=48) for 48 weeks. At Week 48, 89% of subjects in the VIREAD treatment group and 90% of subjects in the d4T or AZT treatment group had HIV-1 RNA concentrations <400 copies/mL. Trial 321 was a placebo-controlled trial in 87 HIV-1 treatment experienced subjects 12 years to less than 18 years of age who were treated with VIREAD (N=45) or placebo (N=42) in combination with an optimized background regimen for 48 weeks. Overall, the trial failed to show a difference in virologic response between the VIREAD and placebo groups. Subgroup analyses suggest the lack of difference in virologic response may be attributable to imbalances between treatment arms in baseline viral susceptibility to VIREAD and OBR [see Adverse Reactions (6.1) and Clinical Studies (14.3)].

Although changes in HIV-1 RNA in these highly treatment-experienced subjects in Trial 321 were less than anticipated, the pharmacokinetic profile of tenofovir in patients 2 years to less than 18 years of age at the recommended doses was similar to that found to be safe and effective in adult clinical trials [see Clinical Pharmacology (12.3)].

The effects of VIREAD-associated changes in BMD and biochemical markers on long-term bone health and future fracture risk in HIV-1 pediatric patients 2 years and older are unknown. The long-term effect of lower spine and total body BMD on skeletal growth in pediatric patients 2 years and older, and in particular, the effects of long-duration exposure in younger children is unknown [see Warnings and Precautions (5.5), Adverse Reactions (6.1)].

Safety and effectiveness of VIREAD in pediatric patients younger than 2 years of age and weighing less than 10 kg with HIV-1 infection have not been established.

Pediatric Patients 2 Years of Age and Older with Chronic Hepatitis B

The safety and effectiveness of VIREAD in pediatric patients 2 years to less than 18 years of age is supported by data from two randomized trials (Trial 115 and Trial 144) in which VIREAD was administered to HBV-infected treatment-experienced subjects.

In Trial 115, 106 HBeAg negative (9%) and positive (91%) subjects 12 years to less than 18 years of age with chronic HBV infection were randomized to receive blinded treatment with VIREAD or placebo for 72 weeks. At Week 72, 88% of subjects in the VIREAD group and 0% of subjects in the placebo group had HBV DNA <400 copies/mL (69 IU/mL). In Trial 144, 89 HBeAg positive (96%) and negative (4%) subjects 2 years to less than 12 years of age were treated with VIREAD 8 mg/kg up to maximum dose of 300 mg or placebo once daily for 48 weeks. At Week 48, 77% of subjects in the VIREAD group and 7% of subjects in the placebo group had HBV DNA <400 copies/mL (69 IU/mL).

The effects of VIREAD-associated changes in BMD and biochemical markers on long-term bone health and future fracture risk in chronic HBV-infected pediatric patients 2 years and older are unknown. The long-term effect of lower spine and total body BMD on skeletal growth in pediatric patients 2 years and older, and in particular, the effects of long-duration exposure in younger children is unknown [see Warnings and Precautions (5.5), Adverse Reactions (6.1)].

Safety and effectiveness of VIREAD in chronic HBV-infected pediatric patients younger than 2 years of age and weighing less than 10 kg have not been established.

8.5 Geriatric Use

Clinical trials of VIREAD did not include sufficient numbers of subjects aged 65 and over to determine whether they respond differently from younger subjects. In general, dose selection for the elderly patient should be cautious, keeping in mind the greater frequency of decreased hepatic, renal, or cardiac function, and of concomitant disease or other drug therapy.

8.6 Renal Impairment

The dosing interval for VIREAD should be modified in adult patients with estimated creatinine clearance below 50 mL/min or in patients with end stage renal disease requiring dialysis [see Dosage and Administration (2.4) and Clinical Pharmacology (12.3)].

10 OVERDOSAGE

If overdose occurs, the patient must be monitored for evidence of toxicity, and standard supportive treatment applied as necessary.

Tenofovir is efficiently removed by hemodialysis with an extraction coefficient of approximately 54%. Following a single 300 mg dose of VIREAD, a four-hour hemodialysis session removed approximately 10% of the administered tenofovir dose.

11 DESCRIPTION

VIREAD is the brand name for tenofovir disoproxil fumarate (TDF) (a prodrug of tenofovir) which is a fumaric acid salt of bis-isopropoxycarbonyloxymethyl ester derivative of tenofovir. TDF is converted in vivo to tenofovir, an acyclic nucleoside phosphonate (nucleotide) analog of adenosine 5'-monophosphate. Tenofovir exhibits activity against HIV-1 reverse transcriptase.

The chemical name of TDF is 9-[(R)-2-[[bis[[(isopropoxycarbonyl)oxy]methoxy]phosphinyl]methoxy]propyl]adenine fumarate (1:1). It has a molecular formula of C19H30N5O10P ∙ C4H4O4 and a molecular weight of 635.52. It has the following structural formula:

Tenofovir disoproxil fumarate is a white to off-white crystalline powder with a solubility of 13.4 mg/mL in distilled water at 25 °C. It has an octanol/phosphate buffer (pH 6.5) partition coefficient (log p) of 1.25 at 25 °C.

VIREAD is available as tablets or as an oral powder.

VIREAD tablets are for oral administration and are available in the following strengths: 150 mg, 200 mg, 250 mg, and 300 mg of TDF (equivalent to 123 mg, 163 mg, 204 mg, and 245 mg of tenofovir disoproxil, respectively).

All strengths of VIREAD tablets contain the following inactive ingredients: croscarmellose sodium, lactose monohydrate, magnesium stearate, microcrystalline cellulose, and pregelatinized starch. The 300 mg strength tablets are coated with Opadry II Y-30-10671-A, which contains FD&C blue #2 aluminum lake, hypromellose 2910, lactose monohydrate, titanium dioxide, and triacetin. The 150 mg, 200 mg, and 250 mg strength tablets are coated with Opadry II 32K-18425, which contains hypromellose 2910, lactose monohydrate, titanium dioxide, and triacetin.

VIREAD oral powder is available for oral administration as white, taste-masked, coated granules containing 40 mg of TDF per gram of oral powder (equivalent to 33 mg of tenofovir disoproxil). The oral powder contains the following inactive ingredients: mannitol, hydroxypropyl cellulose, ethylcellulose, and silicon dioxide.

In this insert, all dosages are expressed in terms of TDF except where otherwise noted.

12 CLINICAL PHARMACOLOGY

12.1 Mechanism of Action

Tenofovir disoproxil fumarate is an antiviral drug [see Microbiology (12.4)].

12.3 Pharmacokinetics

The pharmacokinetics of TDF have been evaluated in healthy volunteers and HIV-1 infected individuals. Tenofovir pharmacokinetics are similar between these populations.

Absorption

VIREAD is a water soluble diester prodrug of the active ingredient tenofovir. The oral bioavailability of tenofovir from VIREAD in fasted subjects is approximately 25%. Following oral administration of a single dose of VIREAD 300 mg to HIV-1 infected subjects in the fasted state, maximum serum concentrations (Cmax) are achieved in 1.0 ± 0.4 hrs. Cmax and AUC values are 0.30 ± 0.09 µg/mL and 2.29 ± 0.69 µg∙hr/mL, respectively.

The pharmacokinetics of tenofovir are dose proportional over a VIREAD dose range of 75 to 600 mg and are not affected by repeated dosing.

In a single-dose bioequivalence study conducted under non-fasted conditions (dose administered with 4 oz. applesauce) in healthy adult volunteers, the mean Cmax of tenofovir was 26% lower for the oral powder relative to the tablet formulation. Mean AUC of tenofovir was similar between the oral powder and tablet formulations.

Distribution

In vitro binding of tenofovir to human plasma or serum proteins is less than 0.7 and 7.2%, respectively, over the tenofovir concentration range 0.01 to 25 µg/mL. The volume of distribution at steady-state is 1.3 ± 0.6 L/kg and 1.2 ± 0.4 L/kg, following intravenous administration of tenofovir 1.0 mg/kg and 3.0 mg/kg.

Metabolism and Elimination

In vitro studies indicate that neither tenofovir disoproxil nor tenofovir are substrates of CYP enzymes.

Following IV administration of tenofovir, approximately 70–80% of the dose is recovered in the urine as unchanged tenofovir within 72 hours of dosing. Following single dose, oral administration of VIREAD, the terminal elimination half-life of tenofovir is approximately 17 hours. After multiple oral doses of VIREAD 300 mg once daily (under fed conditions), 32 ± 10% of the administered dose is recovered in urine over 24 hours.

Tenofovir is eliminated by a combination of glomerular filtration and active tubular secretion. There may be competition for elimination with other compounds that are also renally eliminated.

Effects of Food on Oral Absorption

Administration of VIREAD 300 mg tablets following a high-fat meal (~700 to 1,000 kcal containing 40 to 50% fat) increases the oral bioavailability, with an increase in tenofovir AUC0–∞ of approximately 40% and an increase in Cmax of approximately 14%. However, administration of VIREAD with a light meal did not have a significant effect on the pharmacokinetics of tenofovir when compared to fasted administration of the drug. Food delays the time to tenofovir Cmax by approximately 1 hour. Cmax and AUC of tenofovir are 0.33 ± 0.12 µg/mL and 3.32 ± 1.37 µg∙hr/mL following multiple doses of VIREAD 300 mg once daily in the fed state, when meal content was not controlled.

Specific Populations

Race

There were insufficient numbers from racial and ethnic groups other than Caucasian to adequately determine potential pharmacokinetic differences among these populations.

Gender

Tenofovir pharmacokinetics are similar in male and female subjects.

Pediatric Patients

2 Years and Older: Steady-state pharmacokinetics of tenofovir were evaluated in 31 HIV-1 infected pediatric subjects 2 years to less than 18 years of age (Table 13). Tenofovir exposure achieved in these pediatric subjects receiving oral once daily doses of VIREAD 300 mg (tablet) or 8 mg/kg of body weight (powder) up to a maximum dose of 300 mg was similar to exposures achieved in adults receiving once-daily doses of VIREAD 300 mg.

Table 13 Mean (± SD) Tenofovir Pharmacokinetic Parameters by Age Groups for HIV-1 infected Pediatric Patients 2 years and older for the Tablet and Oral Powder
Dose and Formulation | 300 mg Tablet | 8 mg/kg Oral Powder
 | 12 Years to <18 Years (N=8) | 2 Years to <12 Years (N=23)
Cmax (µg/mL) | 0.38 ± 0.13 | 0.24 ± 0.13
AUCtau (µg∙hr/mL) | 3.39 ± 1.22 | 2.59 ± 1.06

Tenofovir exposures in HBV-infected pediatric subjects (12 years to less than 18 years of age) receiving oral once-daily doses of VIREAD 300 mg tablet and pediatric subjects 2 years to less than 12 years of age receiving VIREAD 8 mg/kg of body weight (tablet or powder) up to a maximum dose of 300 mg were comparable to exposures achieved in HIV-1 infected adult subjects receiving identical doses.

Geriatric Patients

Pharmacokinetic trials have not been performed in the elderly (65 years and older).

Patients with Renal Impairment

The pharmacokinetics of tenofovir are altered in subjects with renal impairment [see Warnings and Precautions (5.2)]. In subjects with creatinine clearance below 50 mL/min or with end-stage renal disease (ESRD) requiring dialysis, Cmax, and AUC0–∞ of tenofovir were increased (Table 14).

Table 14 Pharmacokinetic Parameters (Mean ± SD) of Tenofovir [300 mg, single dose of VIREAD] in Subjects with Varying Degrees of Renal Function
Baseline Creatinine Clearance (mL/min) | >80 N=3 | 50–80 N=10 | 30–49 N=8 | 12–29 N=11
Cmax (µg/mL) | 0.34 ± 0.03 | 0.33 ± 0.06 | 0.37 ± 0.16 | 0.60 ± 0.19
AUC0–∞ (µg∙hr/mL) | 2.18 ± 0.26 | 3.06 ± 0.93 | 6.01 ± 2.50 | 15.98 ± 7.22
CL/F (mL/min) | 1043.7 ± 115.4 | 807.7 ± 279.2 | 444.4 ± 209.8 | 177.0 ± 97.1
CLrenal (mL/min) | 243.5 ± 33.3 | 168.6 ± 27.5 | 100.6 ± 27.5 | 43.0 ± 31.2

Patients with Hepatic Impairment

The pharmacokinetics of tenofovir following a 300 mg single dose of VIREAD have been studied in non-HIV infected subjects with moderate to severe hepatic impairment. There were no substantial alterations in tenofovir pharmacokinetics in subjects with hepatic impairment compared with unimpaired subjects. No change in VIREAD dosing is required in patients with hepatic impairment.

Assessment of Drug Interactions

At concentrations substantially higher (~300-fold) than those observed in vivo, tenofovir did not inhibit in vitro drug metabolism mediated by any of the following human CYP isoforms: CYP3A4, CYP2D6, CYP2C9, or CYP2E1. However, a small (6%) but statistically significant reduction in metabolism of CYP1A substrate was observed. Based on the results of in vitro experiments and the known elimination pathway of tenofovir, the potential for CYP-mediated interactions involving tenofovir with other medicinal products is low.

VIREAD has been evaluated in healthy volunteers in combination with other antiretroviral and potential concomitant drugs. Tables 15 and 16 summarize pharmacokinetic effects of coadministered drug on tenofovir pharmacokinetics and effects of VIREAD on the pharmacokinetics of coadministered drug.

TDF is a substrate of P-glycoprotein (P-gp) and breast cancer resistance protein (BCRP) transporters. When TDF is coadministered with an inhibitor of these transporters, an increase in absorption may be observed.

No clinically significant drug interactions have been observed between VIREAD and efavirenz, methadone, nelfinavir, oral contraceptives, ribavirin, or sofosbuvir.

Table 15 Drug Interactions: Changes in Pharmacokinetic Parameters for Tenofovir [Subjects received VIREAD 300 mg once daily.] in the Presence of the Coadministered Drug
Coadministered Drug | Dose of Coadministered Drug (mg) | N | % Change of Tenofovir Pharmacokinetic Parameters [Increase = ↑; Decrease = ↓; No Effect = ⇔] (90% CI)
Coadministered Drug | Dose of Coadministered Drug (mg) | N | Cmax | AUC | Cmin
Atazanavir [Reyataz Prescribing Information.] | 400 once daily × 14 days | 33 | ↑ 14 (↑ 8 to ↑ 20) | ↑ 24 (↑ 21 to ↑ 28) | ↑ 22 (↑ 15 to ↑ 30)
Atazanavir/ Ritonavir | 300/100 once daily | 12 | ↑ 34 (↑ 20 to ↑ 51) | ↑ 37 (↑ 30 to ↑ 45) | ↑ 29 (↑ 21 to ↑ 36)
Darunavir/ Ritonavir [Prezista Prescribing Information.] | 300/100 twice daily | 12 | ↑ 24 (↑ 8 to ↑ 42) | ↑ 22 (↑ 10 to ↑ 35) | ↑ 37 (↑ 19 to ↑ 57)
Indinavir | 800 three times daily × 7 days | 13 | ↑ 14 (↓ 3 to ↑ 33) | ⇔ | ⇔
Ledipasvir/ Sofosbuvir [Data generated from simultaneous dosing with HARVONI (ledipasvir/sofosbuvir). Staggered administration (12 hours apart) provided similar results.] , [Comparison based on exposures when administered as atazanavir/ritonavir + FTC/TDF.] | 90/400 once daily × 10 days | 24 | ↑ 47 (↑ 37 to ↑ 58) | ↑ 35 (↑ 29 to ↑ 42) | ↑ 47 (↑ 38 to ↑ 57)
Ledipasvir/ Sofosbuvir, [Comparison based on exposures when administered as darunavir/ritonavir + FTC/TDF.] | 90/400 once daily × 10 days | 23 | ↑ 64 (↑ 54 to ↑ 74) | ↑ 50 (↑ 42 to ↑ 59) | ↑ 59 (↑ 49 to ↑ 70)
Ledipasvir/ Sofosbuvir [Study conducted with ATRIPLA® (EFV/FTC/TDF) coadministered with HARVONI; coadministration with HARVONI also results in comparable increases in tenofovir exposure when TDF is administered as COMPLERA® (FTC/rilpivirine/TDF), or TRUVADA + dolutegravir.] | 90/400 once daily × 14 days | 15 | ↑ 79 (↑ 56 to ↑ 104) | ↑ 98 (↑ 77 to ↑ 123) | ↑ 163 (↑ 132 to↑ 197)
Lopinavir/ Ritonavir | 400/100 twice daily × 14 days | 24 | ⇔ | ↑ 32 (↑ 25 to ↑ 38) | ↑ 51 (↑ 37 to ↑ 66)
Saquinavir/ Ritonavir | 1000/100 twice daily × 14 days | 35 | ⇔ | ⇔ | ↑ 23 (↑ 16 to ↑ 30)
Sofosbuvir [Study conducted with ATRIPLA coadministered with SOVALDI® (sofosbuvir).] | 400 single dose | 16 | ↑ 25 (↑ 8 to ↑ 45) | ⇔ | ⇔
Sofosbuvir/ Velpatasvir [Study conducted with COMPLERA coadministered with EPCLUSA; coadministration with EPCLUSA also results in comparable increases in tenofovir exposures when TDF is administered as ATRIPLA, STRIBILD® (elvitegravir/cobicistat/FTC/TDF), TRUVADA + atazanavir/ritonavir, or TRUVADA + darunavir/ritonavir.] | 400/100 once daily | 24 | ↑ 44 (↑ 33 to ↑ 55) | ↑ 40 (↑ 34 to ↑ 46) | ↑ 84 (↑ 76 to ↑ 92)
Sofosbuvir/ Velpatasvir [Administered as raltegravir + FTC/TDF.] | 400/100 once daily | 30 | ↑ 46 (↑ 39 to ↑ 54) | ↑ 40 (↑ 34 to ↑ 45) | ↑ 70 (↑ 61 to ↑ 79)
Sofosbuvir/ Velpatasvir/ Voxilaprevir [Comparison based on exposures when administered as darunavir + ritonavir + FTC/TDF.] | 400/100/100 + Voxilaprevir [Study conducted with additional voxilaprevir 100 mg to achieve voxilaprevir exposures expected in HCV-infected patients.] 100 once daily | 29 | ↑ 48 (↑ 36 to ↑ 61) | ↑ 39 (↑ 32 to ↑ 46) | ↑ 47 (↑ 38 to ↑ 56)
Tacrolimus | 0.05 mg/kg twice daily × 7 days | 21 | ↑ 13 (↑ 1 to ↑ 27) | ⇔ | ⇔
Tipranavir/ Ritonavir [Aptivus Prescribing Information.] | 500/100 twice daily | 22 | ↓ 23 (↓ 32 to ↓ 13) | ↓ 2 (↓ 9 to ↑ 5) | ↑ 7 (↓ 2 to ↑ 17)
Tipranavir/ Ritonavir [Aptivus Prescribing Information.] | 750/200 twice daily (23 doses) | 20 | ↓ 38 (↓ 46 to ↓ 29) | ↑ 2 (↓ 6 to ↑ 10) | ↑ 14 (↑ 1 to ↑ 27)

No effect on the pharmacokinetic parameters of the following coadministered drugs was observed with VIREAD: abacavir, didanosine (buffered tablets), emtricitabine, entecavir, and lamivudine.

Table 16 Drug Interactions: Changes in Pharmacokinetic Parameters for Coadministered Drug in the Presence of VIREAD
Coadministered Drug | Dose of Coadministered Drug (mg) | N | % Change of Coadministered Drug Pharmacokinetic Parameters [Increase = ↑; Decrease = ↓; No Effect = ⇔; NA = Not Applicable] (90% CI)
Coadministered Drug | Dose of Coadministered Drug (mg) | N | Cmax | AUC | Cmin
Abacavir | 300 once | 8 | ↑ 12 (↓ 1 to ↑ 26) | ⇔ | NA
Atazanavir [Reyataz Prescribing Information.] | 400 once daily × 14 days | 34 | ↓ 21 (↓ 27 to ↓ 14) | ↓ 25 (↓ 30 to ↓ 19) | ↓ 40 (↓ 48 to ↓ 32)
Atazanavir | Atazanavir/ Ritonavir 300/100 once daily × 42 days | 10 | ↓ 28 (↓ 50 to ↑ 5) | ↓ 25 [In HIV-infected subjects, addition of TDF to atazanavir 300 mg plus ritonavir 100 mg, resulted in AUC and Cmin values of atazanavir that were 2.3- and 4-fold higher than the respective values observed for atazanavir 400 mg when given alone.] (↓ 42 to ↓ 3) | ↓ 23 (↓ 46 to ↑ 10)
Darunavir [Prezista Prescribing Information.] | Darunavir/Ritonavir 300/100 once daily | 12 | ↑ 16 (↓ 6 to ↑ 42) | ↑ 21 (↓ 5 to ↑ 54) | ↑ 24 (↓ 10 to ↑ 69)
Didanosine [Videx EC Prescribing Information. Subjects received didanosine enteric-coated capsules.] | 250 once, simultaneously with VIREAD and a light meal [373 kcal, 8.2 g fat] | 33 | ↓ 20 [Compared with didanosine (enteric-coated) 400 mg administered alone under fasting conditions.] (↓ 32 to ↓ 7) | ⇔ | NA
Emtricitabine | 200 once daily × 7 days | 17 | ⇔ | ⇔ | ↑ 20 (↑ 12 to ↑ 29)
Entecavir | 1 mg once daily × 10 days | 28 | ⇔ | ↑ 13 (↑ 11 to ↑ 15) | ⇔
Indinavir | 800 three times daily × 7 days | 12 | ↓ 11 (↓ 30 to ↑ 12) | ⇔ | ⇔
Lamivudine | 150 twice daily × 7 days | 15 | ↓ 24 (↓ 34 to ↓ 12) | ⇔ | ⇔
Lopinavir | Lopinavir/Ritonavir 400/100 twice daily × 14 days | 24 | ⇔ | ⇔ | ⇔
Ritonavir | Lopinavir/Ritonavir 400/100 twice daily × 14 days | 24 | ⇔ | ⇔ | ⇔
Saquinavir | Saquinavir/Ritonavir 1000/100 twice daily × 14 days | 32 | ↑ 22 (↑ 6 to ↑ 41) | ↑ 29 [Increases in AUC and Cmin are not expected to be clinically relevant; hence no dose adjustments are required when TDF and ritonavir-boosted saquinavir are coadministered.] (↑ 12 to ↑ 48) | ↑ 47 (↑ 23 to ↑ 76)
Ritonavir | Saquinavir/Ritonavir 1000/100 twice daily × 14 days | 32 | ⇔ | ⇔ | ↑ 23 (↑ 3 to ↑ 46)
Tacrolimus | 0.05 mg/kg twice daily × 7 days | 21 | ⇔ | ⇔ | ⇔
Tipranavir [Aptivus Prescribing Information.] | Tipranavir/Ritonavir 500/100 twice daily | 22 | ↓ 17 (↓ 26 to ↓ 6) | ↓ 18 (↓ 25 to ↓ 9) | ↓ 21 (↓ 30 to ↓ 10)
Tipranavir [Aptivus Prescribing Information.] | Tipranavir/Ritonavir 750/200 twice daily (23 doses) | 20 | ↓ 11 (↓ 16 to ↓ 4) | ↓ 9 (↓ 15 to ↓ 3) | ↓ 12 (↓ 22 to 0)

12.4 Microbiology

Mechanism of Action

Tenofovir disoproxil fumarate is an acyclic nucleoside phosphonate diester analog of adenosine monophosphate. Tenofovir disoproxil fumarate requires initial diester hydrolysis for conversion to tenofovir and subsequent phosphorylations by cellular enzymes to form tenofovir diphosphate (TFV-DP), an obligate chain terminator. Tenofovir diphosphate inhibits the activity of HIV-1 reverse transcriptase (RT) and HBV RT by competing with the natural substrate deoxyadenosine 5'-triphosphate and, after incorporation into DNA, by DNA chain termination. Tenofovir diphosphate is a weak inhibitor of mammalian DNA polymerases α, β, and mitochondrial DNA polymerase γ.

Activity against HIV

Antiviral Activity

The antiviral activity of tenofovir against laboratory and clinical isolates of HIV-1 was assessed in lymphoblastoid cell lines, primary monocyte/macrophage cells and peripheral blood lymphocytes. The EC50 (50% effective concentration) values for tenofovir were in the range of 0.04 µM to 8.5 µM. In drug combination studies, tenofovir was not antagonistic with HIV-1 NRTIs (abacavir, didanosine, lamivudine, stavudine, zidovudine), NNRTIs (efavirenz, nevirapine), and protease inhibitors (amprenavir, indinavir, nelfinavir, ritonavir, saquinavir). Tenofovir displayed antiviral activity in cell culture against HIV-1 clades A, B, C, D, E, F, G, and O (EC50 values ranged from 0.5 µM to 2.2 µM) and strain-specific activity against HIV-2 (EC50 values ranged from 1.6 µM to 5.5 µM).

Resistance

HIV-1 isolates with reduced susceptibility to tenofovir have been selected in cell culture. These viruses expressed a K65R substitution in RT and showed a 2- to 4-fold reduction in susceptibility to tenofovir. In addition, a K70E substitution in HIV-1 RT has been selected by tenofovir and results in low-level reduced susceptibility to tenofovir.

In Trial 903 of treatment-naïve subjects (VIREAD+3TC+EFV versus d4T+3TC+EFV) [see Clinical Studies (14.2)], genotypic analyses of isolates from subjects with virologic failure through Week 144 showed development of EFV and 3TC resistance-associated substitutions to occur most frequently and with no difference between the treatment arms. The K65R substitution occurred in 8/47 (17%) of analyzed patient isolates in the VIREAD arm and in 2/49 (4%) of analyzed patient isolates in the d4T arm. Of the 8 subjects whose virus developed K65R in the VIREAD arm through 144 weeks, 7 occurred in the first 48 weeks of treatment and one at Week 96. One patient in the VIREAD arm developed the K70E substitution in the virus. Other substitutions resulting in resistance to VIREAD were not identified in this trial.

In Trial 934 of treatment-naïve subjects (VIREAD+FTC+EFV versus AZT/3TC+EFV) [see Clinical Studies (14.2)], genotypic analysis performed on HIV-1 isolates from all confirmed virologic failure subjects with >400 copies/mL of HIV-1 RNA at Week 144 or early discontinuation showed development of EFV resistance-associated substitutions occurred most frequently and was similar between the two treatment arms. The M184V substitution, associated with resistance to FTC and 3TC, was observed in 2/19 of analyzed subject isolates in the VIREAD+FTC group and in 10/29 of analyzed subject isolates in the AZT/3TC group. Through 144 weeks of Trial 934, no subjects have developed a detectable K65R substitution in their HIV-1 as analyzed through standard genotypic analysis.

Cross Resistance

Cross resistance among certain HIV-1 NRTIs has been recognized. The K65R and K70E substitutions selected by tenofovir are also selected in some HIV-1 infected subjects treated with abacavir or didanosine. HIV-1 isolates with this substitution also show reduced susceptibility to FTC and 3TC. Therefore, cross resistance among these drugs may occur in patients whose virus harbors the K65R or K70E substitution. HIV-1 isolates from subjects (N=20) whose HIV-1 expressed a mean of three AZT-associated RT substitutions (M41L, D67N, K70R, L210W, T215Y/F, or K219Q/E/N), showed a 3.1-fold decrease in the susceptibility to tenofovir.

In Trials 902 and 907 conducted in treatment-experienced subjects (VIREAD + Standard Background Therapy (SBT) compared to placebo + SBT) [see Clinical Studies (14.2)], 14/304 (5%) of the VIREAD-treated subjects with virologic failure through Week 96 had >1.4-fold (median 2.7-fold) reduced susceptibility to tenofovir. Genotypic analysis of the baseline and failure isolates showed the development of the K65R substitution in the HIV-1 RT gene.

The virologic response to VIREAD therapy has been evaluated with respect to baseline viral genotype (N=222) in treatment-experienced subjects participating in Trials 902 and 907. In these clinical trials, 94% of the participants evaluated had baseline HIV-1 isolates expressing at least one NRTI substitution. Virologic responses for subjects in the genotype substudy were similar to the overall trial results.

Several exploratory analyses were conducted to evaluate the effect of specific substitutions and substitutional patterns on virologic outcome. Because of the large number of potential comparisons, statistical testing was not conducted. Varying degrees of cross resistance of VIREAD to pre-existing AZT resistance-associated substitutions (M41L, D67N, K70R, L210W, T215Y/F, or K219Q/E/N) were observed and appeared to depend on the type and number of specific substitutions. VIREAD-treated subjects whose HIV-1 expressed 3 or more AZT resistance-associated substitutions that included either the M41L or L210W RT substitution showed reduced responses to VIREAD therapy; however, these responses were still improved compared with placebo. The presence of the D67N, K70R, T215Y/F, or K219Q/E/N substitution did not appear to affect responses to VIREAD therapy. Subjects whose virus expressed an L74V substitution without AZT resistance-associated substitutions (N=8) had reduced response to VIREAD. Limited data are available for subjects whose virus expressed a Y115F substitution (N=3), Q151M substitution (N=2), or T69 insertion (N=4), all of whom had a reduced response.

In the protocol defined analyses, virologic response to VIREAD was not reduced in subjects with HIV-1 that expressed the abacavir/FTC/3TC resistance-associated M184V substitution. HIV-1 RNA responses among these subjects were durable through Week 48.

Trials 902 and 907 Phenotypic Analyses

Phenotypic analysis of baseline HIV-1 from treatment-experienced subjects (N=100) demonstrated a correlation between baseline susceptibility to VIREAD and response to VIREAD therapy. Table 17 summarizes the HIV-1 RNA response by baseline VIREAD susceptibility.

Table 17 HIV-1 RNA Response at Week 24 by Baseline VIREAD Susceptibility (Intent-To-Treat) [Tenofovir susceptibility was determined by recombinant phenotypic Antivirogram assay (Virco).]
Baseline VIREAD Susceptibility [Fold change in susceptibility from wild-type.] | Change in HIV-1 RNA [Average HIV-1 RNA change from baseline through Week 24 (DAVG24) in log10 copies/mL.] (N)
<1 | −0.74 (35)
>1 and ≤3 | −0.56 (49)
>3 and ≤4 | −0.3 (7)
>4 | −0.12 (9)

Activity against HBV

Antiviral Activity

The antiviral activity of tenofovir against HBV was assessed in the HepG2 2.2.15 cell line. The EC50 values for tenofovir ranged from 0.14 to 1.5 µM, with CC50 (50% cytotoxicity concentration) values >100 µM. In cell culture combination antiviral activity studies of tenofovir with HBV NrtIs entecavir, lamivudine, and telbivudine, and with the HIV-1 NRTI emtricitabine, no antagonistic activity was observed.

Resistance

Cumulative VIREAD genotypic resistance has been evaluated annually for up to 384 weeks in Trials 0102, 0103, 0106, 0108, and 0121 [see Clinical Studies (14.4)] with the paired HBV rt amino acid sequences of the pretreatment and on-treatment isolates from subjects who received at least 24 weeks of VIREAD monotherapy and remained viremic with HBV DNA ≥400 copies/mL (69 IU/mL) at the end of each study year (or at discontinuation of VIREAD monotherapy) using an as-treated analysis. In the nucleotide-naïve population from Trials 0102 and 0103, HBeAg-positive subjects had a higher baseline viral load than HBeAg-negative subjects and a significantly higher proportion of the subjects remained viremic at their last time point on VIREAD monotherapy (15% versus 5%, respectively).

HBV isolates from these subjects who remained viremic showed treatment-emergent substitutions (Table 18); however, no specific substitutions occurred at a sufficient frequency to be associated with resistance to VIREAD (genotypic and phenotypic analyses).

Table 18 Amino Acid Substitutions in Viremic Subjects across HBV Trials of VIREAD
 | Compensated Liver Disease
 | Nucleotide-Naïve (N=417) [Nucleotide-naïve subjects from Trials 0102 (N=246) and 0103 (N=171) receiving up to 384 weeks of treatment with VIREAD.] | HEPSERA-Experienced (N=247) [HEPSERA-experienced subjects from Trials 0102/0103 (N=195) and 0106 (N=52) receiving up to 336 weeks of treatment with VIREAD after switching to VIREAD from HEPSERA. Trial 0106, a randomized, double-blind, 168-week Phase 2 trial, has been completed.] | Lamivudine- Resistant (N=136) [Lamivudine-resistant subjects from Trial 0121 (N=136) receiving up to 96 weeks of treatment with VIREAD after switching to VIREAD from lamivudine.] | Decompensated Liver Disease (N=39) [Subjects with decompensated liver disease from Trial 0108 (N=39) receiving up to 48 weeks of treatment with VIREAD.]
Viremic at Last Time Point on VIREAD | 38/417 (9%) | 37/247 (15%) | 9/136 (7%) | 7/39 (18%)
Treatment-Emergent Amino Acid Substitutions [Denominator includes those subjects who were viremic at last time point on VIREAD monotherapy and had evaluable paired genotypic data.] | 18 [Of the 18 subjects with treatment-emergent amino acid substitutions during Trials 0102 and 0103, 5 subjects had substitutions at conserved sites and 13 subjects had substitutions only at polymorphic sites, and 8 subjects had only transient substitutions that were not detected at the last time point on VIREAD.] /32 (56%) | 11 [Of the 11 HEPSERA-experienced subjects with treatment-emergent amino acid substitutions, 2 subjects had substitutions at conserved sites and 9 had substitutions only at polymorphic sites.] /31 (35%) | 6 [Of the 6 lamivudine-resistant subjects with treatment-emergent substitutions during Trial 0121, 3 subjects had substitutions at conserved sites and 3 had substitutions only at polymorphic sites.] /8 (75%) | 3/5 (60%)

Cross Resistance

Cross resistance has been observed between HBV NrtIs.

In cell-based assays, HBV strains expressing the rtV173L, rtL180M, and rtM204I/V substitutions associated with resistance to lamivudine (3TC) and telbivudine showed a susceptibility to tenofovir ranging from 0.7- to 3.4-fold that of wild type virus. The rtL180M and rtM204I/V double substitutions conferred 3.4-fold reduced susceptibility to tenofovir.

HBV strains expressing the rtL180M, rtT184G, rtS202G/I, rtM204V, and rtM250V substitutions associated with resistance to entecavir showed a susceptibility to tenofovir ranging from 0.6- to 6.9-fold that of wild type virus.

HBV strains expressing the adefovir resistance-associated substitutions rtA181V and/or rtN236T showed reductions in susceptibility to tenofovir ranging from 2.9- to 10-fold that of wild type virus. Strains containing the rtA181T substitution showed changes in susceptibility to tenofovir ranging from 0.9- to 1.5-fold that of wild type virus.

One hundred fifty-two subjects initiating VIREAD therapy in Trials 0102, 0103, 0106, 0108, and 0121 harbored HBV with known resistance substitutions to HBV NrtIs: 14 with adefovir resistance-associated substitutions (rtA181S/T/V and/or rtN236T), 135 with 3TC resistance-associated substitutions (rtM204I/V), and 3 with both adefovir and 3TC resistance-associated substitutions. Following up to 384 weeks of VIREAD treatment, 10 of the 14 subjects with adefovir-resistant HBV, 124 of the 135 subjects with 3TC-resistant HBV, and 2 of the 3 subjects with both adefovir- and 3TC-resistant HBV achieved and maintained virologic suppression (HBV DNA <400 copies/mL [69 IU/mL]). Three of the 5 subjects whose virus harbored both the rtA181T/V and rtN236T substitutions remained viremic.

13 NONCLINICAL TOXICOLOGY

13.1 Carcinogenesis, Mutagenesis, Impairment of Fertility

Carcinogenesis

Long-term oral carcinogenicity studies of TDF in mice and rats were carried out at exposures up to approximately 16 times (mice) and 5 times (rats) those observed in humans at the therapeutic dose for HIV-1 infection. At the high dose in female mice, liver adenomas were increased at exposures 16 times that in humans. In rats, the study was negative for carcinogenic findings at exposures up to 5 times that observed in humans at the therapeutic dose.

Mutagenesis

Tenofovir disoproxil fumarate was mutagenic in the in vitro mouse lymphoma assay and negative in an in vitro bacterial mutagenicity test (Ames test). In an in vivo mouse micronucleus assay, TDF was negative when administered to male mice.

Impairment of Fertility

There were no effects on fertility, mating performance or early embryonic development when TDF was administered to male rats at a dose equivalent to 10 times the human dose based on body surface area comparisons for 28 days prior to mating and to female rats for 15 days prior to mating through day seven of gestation. There was, however, an alteration of the estrous cycle in female rats.

13.2 Animal Toxicology and/or Pharmacology

Tenofovir and TDF administered in toxicology studies to rats, dogs, and monkeys at exposures (based on AUCs) greater than or equal to 6 fold those observed in humans caused bone toxicity. In monkeys the bone toxicity was diagnosed as osteomalacia. Osteomalacia observed in monkeys appeared to be reversible upon dose reduction or discontinuation of tenofovir. In rats and dogs, the bone toxicity manifested as reduced bone mineral density. The mechanism(s) underlying bone toxicity is unknown.

Evidence of renal toxicity was noted in 4 animal species. Increases in serum creatinine, BUN, glycosuria, proteinuria, phosphaturia, and/or calciuria and decreases in serum phosphate were observed to varying degrees in these animals. These toxicities were noted at exposures (based on AUCs) 2–20 times higher than those observed in humans. The relationship of the renal abnormalities, particularly the phosphaturia, to the bone toxicity is not known.

14 CLINICAL STUDIES

14.1 Overview of Clinical Trials

The efficacy and safety of VIREAD in adults and pediatric subjects were evaluated in the trials summarized in Table 19.

Table 19 Trials Conducted with VIREAD in Adults and Pediatric Subjects for HIV-1 Treatment and Chronic HBV Treatment
Trial | Population | Study Arms (N) [Randomized and dosed.] | Timepoint (Week)
Trial 903 [Randomized, double-blind, active-controlled trial.] (NCT00158821) | HIV-1 treatment-naïve adults | VIREAD+lamivudine+efavirenz (299) stavudine+lamivudine+efavirenz (301) | 144
Trial 934 [Randomized, open-label active-controlled trial.] (NCT00112047) | HIV-1 treatment-naïve adults | emtricitabine+VIREAD+efavirenz (257) zidovudine/lamivudine+efavirenz (254) | 144
Trial 907 [Randomized, double-blind, placebo-controlled trial.] (NCT00002450) | HIV-1 treatment-experienced adults | VIREAD (368) Placebo (182) | 24
Trial 0102 (NCT00117676) | HBeAg-negative adults with chronic HBV | VIREAD (250) HEPSERA (125) | 48
Trial 0103 (NCT00116805) | HBeAg-positive adults with chronic HBV | VIREAD (176) HEPSERA (90) | 48
Trial 121 (NCT00737568) | Adults with lamivudine-resistant chronic HBV | VIREAD (141) | 96
Trial 0108 (NCT00298363) | Adults with chronic HBV and decompensated liver disease | VIREAD (45) | 48
Trial 352 (NCT00528957) | HIV-1 treatment experienced pediatric subjects 2 years to <12 years | VIREAD (44) stavudine or zidovudine (48) | 48
Trial 321 (NCT00352053) | HIV-1 treatment-experienced pediatric subjects 12 years to <18 years | VIREAD (45) Placebo (42) | 48
Trial 115 (NCT00734162) | Pediatric subjects 12 years to <18 years with chronic HBV | VIREAD (52) Placebo (54) | 72
Trial 144 (NCT01651403) | Pediatric subjects 2 years to <12 years with chronic HBV | VIREAD (60) Placebo (29) | 48

14.2 Clinical Trial Results in Adults with HIV-1 Infection

Treatment-Naïve Subjects: Trial 903

Data through 144 weeks are reported for Trial 903, a double-blind, active-controlled multicenter trial comparing VIREAD (300 mg once daily) administered in combination with lamivudine (3TC) and efavirenz (EFV) versus stavudine (d4T), 3TC, and EFV in 600 antiretroviral-naïve subjects. Subjects had a mean age of 36 years (range 18–64); 74% were male, 64% were Caucasian, and 20% were Black. The mean baseline CD4+ cell count was 279 cells/mm^3 (range 3–956) and median baseline plasma HIV-1 RNA was 77,600 copies/mL (range 417–5,130,000). Subjects were stratified by baseline HIV-1 RNA and CD4+ cell count. Forty-three percent of subjects had baseline viral loads >100,000 copies/mL and 39% had CD4+ cell counts <200 cells/mm^3. Table 20 provides treatment outcomes through 48 and 144 weeks.

Table 20 Outcomes of Randomized Treatment at Week 48 and 144 (Trial 903)
 | At Week 48 |  | At Week 144
Outcomes | VIREAD+3TC+EFV (N=299) | d4T+3TC+EFV (N=301) | VIREAD+3TC+EFV (N=299) | d4T+3TC+EFV (N=301)
Responder [Subjects achieved and maintained confirmed HIV-1 RNA <400 copies/mL through Week 48 and 144.] | 79% | 82% | 68% | 62%
Virologic failure [Includes confirmed viral rebound and failure to achieve confirmed <400 copies/mL through Week 48 and 144.] | 6% | 4% | 10% | 8%
Rebound | 5% | 3% | 8% | 7%
Never suppressed | 0% | 1% | 0% | 0%
Added an antiretroviral agent | 1% | 1% | 2% | 1%
Death | <1% | 1% | <1% | 2%
Discontinued due to adverse event | 6% | 6% | 8% | 13%
Discontinued for other reasons [Includes lost to follow-up, subject's withdrawal, noncompliance, protocol violation and other reasons.] | 8% | 7% | 14% | 15%

Achievement of plasma HIV-1 RNA concentrations of <400 copies/mL at Week 144 was similar between the two treatment groups for the population stratified at baseline on the basis of HIV-1 RNA concentration (> or ≤100,000 copies/mL) and CD4+ cell count (< or ≥200 cells/mm^3). Through 144 weeks of therapy, 62% and 58% of subjects in the VIREAD and d4T arms, respectively, achieved and maintained confirmed HIV-1 RNA <50 copies/mL. The mean increase from baseline in CD4+ cell count was 263 cells/mm^3 for the VIREAD arm and 283 cells/mm^3 for the d4T arm.

Through 144 weeks, 11 subjects in the VIREAD group and 9 subjects in the d4T group experienced a new CDC Class C event.

Treatment-Naïve Subjects: Trial 934

Data through 144 weeks are reported for Trial 934, a randomized, open-label, active-controlled multicenter trial comparing emtricitabine (FTC) + VIREAD administered in combination with efavirenz (EFV) versus zidovudine (AZT)/lamivudine (3TC) fixed-dose combination administered in combination with EFV in 511 antiretroviral-naïve subjects. From Weeks 96 to 144 of the trial, subjects received a fixed-dose combination of FTC and TDF with EFV in place of FTC + VIREAD with EFV. Subjects had a mean age of 38 years (range 18–80); 86% were male, 59% were Caucasian, and 23% were Black. The mean baseline CD4+ cell count was 245 cells/mm^3 (range 2–1191) and median baseline plasma HIV-1 RNA was 5.01 log10 copies/mL (range 3.56–6.54). Subjects were stratified by baseline CD4+ cell count (< or ≥200 cells/mm^3); 41% had CD4+ cell counts <200 cells/mm^3 and 51% of subjects had baseline viral loads >100,000 copies/mL. Table 21 provides treatment outcomes through 48 and 144 weeks for those subjects who did not have EFV resistance at baseline.

Table 21 Outcomes of Randomized Treatment at Week 48 and 144 (Trial 934)
Outcomes | At Week 48 |  | At Week 144
Outcomes | FTC+VIREAD+EFV (N=244) | AZT/3TC+EFV (N=243) | FTC+VIREAD+EFV (N=227) [Subjects who were responders at Week 48 or Week 96 (HIV-1 RNA <400 copies/mL) but did not consent to continue the trial after Week 48 or Week 96 were excluded from analysis.] | AZT/3TC+EFV (N=229)
Responder [Subjects achieved and maintained confirmed HIV-1 RNA <400 copies/mL through Weeks 48 and 144.] | 84% | 73% | 71% | 58%
Virologic failure [Includes confirmed viral rebound and failure to achieve confirmed <400 copies/mL through Weeks 48 and 144.] | 2% | 4% | 3% | 6%
Rebound | 1% | 3% | 2% | 5%
Never suppressed | 0% | 0% | 0% | 0%
Change in antiretroviral regimen | 1% | 1% | 1% | 1%
Death | <1% | 1% | 1% | 1%
Discontinued due to adverse event | 4% | 9% | 5% | 12%
Discontinued for other reasons [Includes lost to follow-up, subject withdrawal, noncompliance, protocol violation and other reasons.] | 10% | 14% | 20% | 22%

Through Week 48, 84% and 73% of subjects in the FTC + VIREAD group and the AZT/3TC group, respectively, achieved and maintained HIV-1 RNA <400 copies/mL (71% and 58% through Week 144). The difference in the proportion of subjects who achieved and maintained HIV-1 RNA <400 copies/mL through 48 weeks largely results from the higher number of discontinuations due to adverse events and other reasons in the AZT/3TC group in this open-label trial. In addition, 80% and 70% of subjects in the FTC + VIREAD group and the AZT/3TC group, respectively, achieved and maintained HIV-1 RNA <50 copies/mL through Week 48 (64% and 56% through Week 144). The mean increase from baseline in CD4+ cell count was 190 cells/mm^3 in the FTC + VIREAD group and 158 cells/mm^3 in the AZT/3TC group at Week 48 (312 and 271 cells/mm^3 at Week 144).

Through 48 weeks, 7 subjects in the FTC + VIREAD group and 5 subjects in the AZT/3TC group experienced a new CDC Class C event (10 and 6 subjects through 144 weeks).

Treatment-Experienced Subjects: Trial 907

Trial 907 was a 24-week, double-blind, placebo-controlled multicenter trial of VIREAD added to a stable background regimen of antiretroviral agents in 550 treatment-experienced subjects. After 24 weeks of blinded trial treatment, all subjects continuing on trial were offered open-label VIREAD for an additional 24 weeks. Subjects had a mean baseline CD4+ cell count of 427 cells/mm^3 (range 23–1,385), median baseline plasma HIV-1 RNA of 2,340 (range 50–75,000) copies/mL, and mean duration of prior HIV-1 treatment was 5.4 years. Mean age of the subjects was 42 years; 85% were male, 69% Caucasian, 17% Black, and 12% Hispanic.

Table 22 provides the percent of subjects with HIV-1 RNA <400 copies/mL and outcomes of subjects through 48 weeks.

Table 22 Outcomes of Randomized Treatment (Trial 907)
Outcomes | 0–24 weeks |  | 0–48 weeks | 24–48 weeks
Outcomes | VIREAD (N=368) | Placebo (N=182) | VIREAD (N=368) | Placebo Crossover to VIREAD (N=170)
HIV-1 RNA <400 copies/mL [Subjects with HIV-1 RNA <400 copies/mL and no prior study drug discontinuation at Week 24 and 48, respectively.] | 40% | 11% | 28% | 30%
Virologic failure [Subjects with HIV-1 RNA ≥400 copies/mL efficacy failure or missing HIV-1 RNA at Week 24 and 48, respectively.] | 53% | 84% | 61% | 64%
Discontinued due to adverse event | 3% | 3% | 5% | 5%
Discontinued for other reasons [Includes lost to follow-up, subject withdrawal, noncompliance, protocol violation, and other reasons.] | 3% | 3% | 5% | 1%

At 24 weeks of therapy, there was a higher proportion of subjects in the VIREAD arm compared to the placebo arm with HIV-1 RNA <50 copies/mL (19% and 1%, respectively). Mean change in absolute CD4+ cell counts by Week 24 was +11 cells/mm^3 for the VIREAD group and −5 cells/mm^3 for the placebo group. Mean change in absolute CD4+ cell counts by Week 48 was +4 cells/mm^3 for the VIREAD group.

Through Week 24, one subject in the VIREAD group and no subjects in the placebo group experienced a new CDC Class C event.

14.3 Clinical Trial Results in Pediatric Subjects with HIV-1 Infection

In Trial 352, 92 treatment-experienced subjects 2 years to less than 12 years of age with stable, virologic suppression on a stavudine (d4T)- or zidovudine (AZT)-containing regimen were randomized to either replace d4T or AZT with VIREAD (N=44) or continue their original regimen (N=48) for 48 weeks. Five additional subjects over the age of 12 years were enrolled and randomized (VIREAD N=4, original regimen N=1) but are not included in the efficacy analysis. After 48 weeks, all eligible subjects were allowed to continue in the trial receiving open-label VIREAD. At Week 48, 89% of subjects in the VIREAD treatment group and 90% of subjects in the d4T or AZT treatment group had HIV-1 RNA concentrations <400 copies/mL. During the 48-week randomized phase of the trial, 1 subject in the VIREAD group discontinued the trial prematurely because of virologic failure/lack of efficacy and 3 subjects (2 subjects in the VIREAD group and 1 subject in the d4T or AZT group) discontinued for other reasons.

In Trial 321, 87 treatment-experienced subjects 12 years to less than 18 years of age were treated with VIREAD (N=45) or placebo (N=42) in combination with an optimized background regimen (OBR) for 48 weeks. The mean baseline CD4 cell count was 374 cells/mm^3 and the mean baseline plasma HIV-1 RNA was 4.6 log10 copies/mL. At baseline, 90% of subjects harbored NRTI resistance-associated substitutions in their HIV-1 isolates. Overall, the trial failed to show a difference in virologic response between the VIREAD and placebo groups. Subgroup analyses suggest the lack of difference in virologic response may be attributable to imbalances between treatment arms in baseline viral susceptibility to VIREAD and OBR.

Although changes in HIV-1 RNA in these highly treatment-experienced subjects were less than anticipated, the comparability of the pharmacokinetic and safety data to that observed in adults supports the use of VIREAD in pediatric patients 12 years and older who weigh at least 35 kg and whose HIV-1 isolate is expected to be sensitive to VIREAD [see Warnings and Precautions (5.5), Adverse Reactions (6.1), and Clinical Pharmacology (12.3)].

14.4 Clinical Trial Results in Adults with Chronic Hepatitis B

HBeAg-Negative Chronic HBV Subjects: Trial 0102

Trial 0102 was a Phase 3, randomized, double-blind, active-controlled trial of VIREAD 300 mg compared to HEPSERA 10 mg in 375 HBeAg- (anti-HBe+) subjects with compensated liver function, the majority of whom were nucleoside-naïve. The mean age of subjects was 44 years; 77% were male, 25% were Asian, 65% were Caucasian, 17% had previously received alpha-interferon therapy, and 18% were nucleoside-experienced (16% had prior lamivudine experience). At baseline, subjects had a mean Knodell necroinflammatory score of 7.8; mean plasma HBV DNA was 6.9 log10 copies/mL; and mean serum ALT was 140 U/L.

HBeAg-Positive Chronic HBV Subjects: Trial 0103

Trial 0103 was a Phase 3, randomized, double-blind, active-controlled trial of VIREAD 300 mg compared to HEPSERA 10 mg in 266 HBeAg+ nucleoside-naïve subjects with compensated liver function. The mean age of subjects was 34 years; 69% were male, 36% were Asian, 52% were Caucasian, 16% had previously received alpha-interferon therapy, and <5% were nucleoside experienced. At baseline, subjects had a mean Knodell necroinflammatory score of 8.4; mean plasma HBV DNA was 8.7 log10 copies /mL; and mean serum ALT was 147 U/L.

The primary data analysis was conducted after all subjects reached 48 weeks of treatment and results are summarized below.

The primary efficacy endpoint in both trials was complete response to treatment defined as HBV DNA <400 copies/mL (69 IU/mL) and Knodell necroinflammatory score improvement of at least 2 points, without worsening in Knodell fibrosis at Week 48 (see Table 23).

Table 23 Histological, Virological, Biochemical, and Serological Response at Week 48 (Trials 0102 and 0103)
 | 0102 (HBeAg-) |  | 0103 (HBeAg+)
 | VIREAD (N=250) | HEPSERA (N=125) | VIREAD (N=176) | HEPSERA (N=90)
Complete Response | 71% | 49% | 67% | 12%
Histology Histological Response [Knodell necroinflammatory score improvement of at least 2 points without worsening in Knodell fibrosis.] | 72% | 69% | 74% | 68%
HBV DNA <400 copies/mL (<69 IU/mL) | 93% | 63% | 76% | 13%
ALT Normalized ALT [The population used for analysis of ALT normalization included only subjects with ALT above ULN at baseline.] | 76% | 77% | 68% | 54%
Serology HBeAg Loss/ Seroconversion | NA [NA = Not Applicable] | NA | 20%/19% | 16%/16%
HBsAg Loss/ Seroconversion | 0/0 | 0/0 | 3%/1% | 0/0

Treatment Beyond 48 Weeks: Trials 0102 and 0103

In Trials 0102 (HBeAg-negative) and 0103 (HBeAg-positive), subjects who completed double-blind treatment (389 and 196 subjects who were originally randomized to VIREAD and HEPSERA, respectively) were eligible to roll over to open-label VIREAD with no interruption in treatment.

In Trial 0102, 266 of 347 subjects who entered the open-label period (77%) continued in the trial through Week 384. Among subjects randomized to VIREAD followed by open-label treatment with VIREAD, 73% had HBV DNA <400 copies/ml (69 IU/ml), and 63% had ALT normalization at Week 384. Among subjects randomized to HEPSERA followed by open-label treatment with VIREAD, 80% had HBV DNA <400 copies/mL (69 IU/mL) and 70% had ALT normalization through Week 384. At Week 384, both HBsAg loss and seroconversion were approximately 1% in both treatment groups.

In Trial 0103, 146 of 238 subjects who entered the open-label period (61%) continued in the trial through Week 384. Among subjects randomized to VIREAD, 49% had HBV DNA <400 copies/mL (69 IU/mL), 42% had ALT normalization, and 20% had HBeAg loss (13% seroconversion to anti-HBe antibody) through Week 384. Among subjects randomized to HEPSERA followed by open-label treatment with VIREAD, 56% had HBV DNA <400 copies/mL (69 IU/mL), 50% had ALT normalization, and 28% had HBeAg loss (19% seroconversion to anti-HBe antibody) through Week 384. At Week 384, HBsAg loss and seroconversion were 11% and 8%, respectively, in subjects initially randomized to VIREAD and 12% and 10%, respectively, in subjects initially randomized to HEPSERA.

Of the originally randomized and treated 641 subjects in the two trials, liver biopsy data from 328 subjects who received continuing open-label treatment with VIREAD monotherapy were available for analysis at baseline, Week 48, and Week 240. There were no apparent differences between the subset of subjects who had liver biopsy data at Week 240 and those subjects remaining on open-label VIREAD without biopsy data that would be expected to affect histological outcomes at Week 240. Among the 328 subjects evaluated, the observed histological response rates were 80% and 88% at Week 48 and Week 240, respectively. In the subjects without cirrhosis at baseline (Ishak fibrosis score 0–4), 92% (216/235) and 95% (223/235) had either improvement or no change in Ishak fibrosis score at Week 48 and Week 240, respectively. In subjects with cirrhosis at baseline (Ishak fibrosis score 5–6), 97% (90/93) and 99% (92/93) had either improvement or no change in Ishak fibrosis score at Week 48 and Week 240, respectively. Twenty-nine percent (27/93) and 72% (67/93) of subjects with cirrhosis at baseline experienced regression of cirrhosis by Week 48 and Week 240, respectively, with a reduction in Ishak fibrosis score of at least 2 points. No definitive conclusions can be established about the remaining study population who were not part of this subset analysis.

Lamivudine-Resistant Chronic HBV Subjects: Trial 121

Trial 121 was a randomized, double-blind, active-controlled trial evaluating the safety and efficacy of VIREAD compared to an unapproved antiviral regimen in subjects with chronic hepatitis B, persistent viremia (HBV DNA ≥1,000 IU/mL), and genotypic evidence of lamivudine resistance (rtM204I/V +/- rtL180M). One hundred forty-one adult subjects were randomized to the VIREAD treatment arm. The mean age of subjects randomized to VIREAD was 47 years (range 18–73); 74% were male, 59% were Caucasian, and 37% were Asian. At baseline, 54% of subjects were HBeAg-negative, 46% were HBeAg-positive, and 56% had abnormal ALT. Subjects had a mean HBV DNA of 6.4 log10 copies/mL and mean serum ALT of 71 U/L at baseline.

After 96 weeks of treatment, 126 of 141 subjects (89%) randomized to VIREAD had HBV DNA <400 copies/mL (69 IU/mL), and 49 of 79 subjects (62%) with abnormal ALT at baseline had ALT normalization. Among the HBeAg-positive subjects randomized to VIREAD, 10 of 65 subjects (15%) experienced HBeAg loss and 7 of 65 subjects (11%) experienced anti-HBe seroconversion through Week 96. The proportion of subjects with HBV DNA concentrations below 400 copies/mL (69 IU/mL) at Week 96 was similar between the VIREAD monotherapy and the comparator arms.

Across the combined chronic hepatitis B treatment trials, the number of subjects with adefovir-resistance associated substitutions at baseline was too small to establish efficacy in this subgroup.

Chronic HBV and Decompensated Liver Disease Subjects: Trial 0108

Trial 0108 was a small randomized, double-blind, active-controlled trial evaluating the safety of VIREAD compared to other antiviral drugs in subjects with chronic hepatitis B and decompensated liver disease through 48 weeks.

Forty-five adult subjects (37 males and 8 females) were randomized to the VIREAD treatment arm. At baseline, 69% of subjects were HBeAg-negative and 31% were HBeAg-positive. Subjects had a mean Child-Pugh score of 7, a mean MELD score of 12, mean HBV DNA of 5.8 log10 copies/mL, and mean serum ALT of 61 U/L at baseline. Trial endpoints were discontinuation due to an adverse event and confirmed increase in serum creatinine ≥0.5 mg/dL or confirmed serum phosphorus of <2 mg/dL [see Adverse Reactions (6.1)].

At 48 weeks, 31/44 (70%) and 12/26 (46%) VIREAD-treated subjects achieved an HBV DNA <400 copies/mL (69 IU/mL), and normalized ALT, respectively. The trial was not designed to evaluate treatment impact on clinical endpoints such as progression of liver disease, need for liver transplantation, or death.

14.5 Clinical Trial Results in Pediatric Subjects with Chronic Hepatitis B

Pediatric Subjects 12 Years to less than 18 Years of Age with Chronic HBV

In Trial 115, 106 HBeAg negative (9%) and positive (91%) subjects aged 12 to less than 18 years with chronic HBV infection were randomized to receive blinded treatment with VIREAD 300 mg (N=52) or placebo (N=54) for 72 weeks. At trial entry, the mean HBV DNA was 8.1 log10 copies/mL and mean ALT was 101 U/L. Of 52 subjects treated with VIREAD, 20 subjects were nucleos(t)ide-naïve and 32 subjects were nucleos(t)ide-experienced. Thirty-one of the 32 nucleos(t)ide-experienced subjects had prior lamivudine experience. At Week 72, 88% (46/52) of subjects in the VIREAD group and 0% (0/54) of subjects in the placebo group had HBV DNA <400 copies/mL (69 IU/mL). Among subjects with abnormal ALT at baseline, 74% (26/35) of subjects receiving VIREAD had normalized ALT at Week 72 compared to 31% (13/42) in the placebo group. One VIREAD-treated subject experienced sustained HBsAg-loss and seroconversion to anti-HBs during the first 72 weeks of trial participation.

Pediatric Subjects 2 Years to less than 12 Years of Age with Chronic HBV

In Trial 144, 89 HBeAg positive (96%) and negative (4%) subjects 2 years to less than 12 years of age with chronic HBV infection were treated with VIREAD 8 mg/kg up to a maximum dose of 300 mg (N=60) or placebo (N=29) once daily for 48 weeks. At trial entry, the mean HBV DNA was 8.1 log10 IU/mL and mean ALT was 123 U/L. There was an overall higher proportion in the VIREAD group with HBV DNA <400 copies/mL (69 IU/mL) and ALT normalization rate at Week 48 compared to the placebo group (Table 24). There was no difference between treatment groups in those who achieved HBeAg loss or HBeAg seroconversion.

Table 24 Outcomes of Randomized Treatment (Trial 144) in Children 2 Years to <12 Years of Age
Endpoint at Week 48 | VIREAD N=60 | Placebo N=29
HBV DNA <400 copies/mL (69 IU/ml) | 46/60 (77%) | 2/29 (7%)
ALT Normalization [Normal ALT was defined as ≤ 34 U/L for females 2–15 years or males 1–9 years old, and ≤ 43 U/L for males 10–15 years. The ALT Normalization analysis excluded 4 treated subjects who had normal ALT at baseline.] | 38/58 (66%) | 4/27 (15%)
HBeAg loss [The analysis excluded 4 subjects who were HBeAg negative and HBeAb positive at baseline.] | 17/56 (30%) | 8/29 (28%)
HBeAg seroconversion | 14/56 (25%) | 7/29 (24%)

In Trials 115 and 144, sequencing data from paired baseline and on treatment HBV isolates from subjects who received VIREAD were available for 14 of 15 subjects who had plasma HBV DNA ≥400 copies/mL. No amino acid substitutions associated with resistance to VIREAD were identified in these isolates by Week 72 (Trial 115) or Week 48 (Trial 144).

16 HOW SUPPLIED/STORAGE AND HANDLING

VIREAD tablets are available in bottles containing 30 tablets with child-resistant closure as follows:

- 150 mg of TDF (equivalent to 123 mg of tenofovir disoproxil): tablets are triangle-shaped, white, film-coated, and debossed with "GSI" on one side and with "150" on the other side. (NDC 61958-0404-1)
- 200 mg of TDF (equivalent to 163 mg of tenofovir disoproxil): tablets are round-shaped, white, film-coated, and debossed with "GSI" on one side and with "200" on the other side. (NDC 61958-0405-1)
- 250 mg of TDF (equivalent to 204 mg of tenofovir disoproxil): tablets are capsule-shaped, white, film-coated and debossed with "GSI" on one side and with "250" on the other side. (NDC 61958-0406-1)
- 300 mg of TDF (equivalent to 245 mg of tenofovir disoproxil): tablets are almond-shaped, light-blue, film-coated, and debossed with "GILEAD" and "4331" on one side and with "300" on the other side. (NDC 61958-0401-1)

VIREAD oral powder consists of white, coated granules containing 40 mg of TDF (equivalent to 33 mg of tenofovir disoproxil) per gram of powder and is available in multi-use bottles containing 60 grams of oral powder, closed with a child-resistant closure, and co-packaged with a dosing scoop. (NDC 61958-0403-1)

STORAGE AND HANDLING

Store VIREAD tablets and oral powder at 25 °C (77 °F), excursions permitted to 15–30 °C (59–86 °F) (see USP Controlled Room Temperature).

- Keep container tightly closed.
- Dispense only in original container.
- Do not use if seal over bottle opening is broken or missing.

17 PATIENT COUNSELING INFORMATION

Advise the patient to read the FDA-approved patient labeling (Patient Information and Instructions for Use).

Severe Acute Exacerbation of Hepatitis B in Patients Infected with HBV

Inform patients that severe acute exacerbations of hepatitis B have been reported in patients infected with hepatitis B virus (HBV) and have discontinued VIREAD. Advise patients not to discontinue VIREAD without first informing their healthcare provider. All patients should be tested for HBV infection before or when starting VIREAD and those who are infected with HBV need close medical follow-up for several months after stopping VIREAD to monitor for exacerbations of hepatitis [see Warnings and Precautions (5.1)].

New Onset or Worsening Renal Impairment

Inform patients that renal impairment, including cases of acute renal failure and Fanconi syndrome, has been reported in association with the use of VIREAD. Advise patients to avoid VIREAD with concurrent or recent use of a nephrotoxic agent (e.g., high-dose or multiple NSAIDs) [see Warnings and Precautions (5.2)]. The dosing interval of VIREAD may need adjustment in HIV-1 infected patients with renal impairment.

Immune Reconstitution Syndrome

Inform patients that in some patients with advanced HIV infection (AIDS) signs and symptoms of inflammation from previous infections may occur soon after anti-HIV treatment is started. It is believed that these symptoms are due to an improvement in the body's immune response, enabling the body to fight infections that may have been present with no obvious symptoms. Advise patients to inform their healthcare provider immediately of any symptoms of infection [see Warnings and Precautions (5.4)].

Bone Loss and Mineralization Defects

Inform patients that decreases in bone mineral density have been observed with the use of VIREAD. Consider bone monitoring in patients who have a history of pathologic bone fracture or at risk for osteopenia [see Warnings and Precautions (5.5)].

Lactic Acidosis and Severe Hepatomegaly

Inform patients that lactic acidosis and severe hepatomegaly with steatosis, including fatal cases, have been reported. Treatment with VIREAD should be suspended in any patient who develops clinical symptoms suggestive of lactic acidosis or pronounced hepatotoxicity [see Warnings and Precautions (5.6)].

Drug Interactions

Advise patients that VIREAD may interact with many drugs; therefore, advise patients to report to their healthcare provider the use of any other medication, including other HIV drugs and drugs for treatment of hepatitis C virus [see Warnings and Precautions (5.7) and Drug Interactions (7)].

Dosing Recommendations

Inform patients that it is important to take VIREAD on a regular dosing schedule with or without food and to avoid missing doses as it can result in development of resistance [see Dosage and Administration (2)].

Pregnancy Registry

Inform patients that there is an antiretroviral pregnancy registry to monitor fetal outcomes of pregnant women exposed to VIREAD [see Use in Specific Populations (8.1)].

Lactation

Instruct mothers not to breastfeed if they are taking VIREAD for the treatment of HIV-1 infection because of the risk of passing the HIV-1 virus to the baby [see Use in Specific Populations (8.2)].

Treatment Duration

Advise patients that in the treatment of chronic hepatitis B, the optimal duration of treatment is unknown. The relationship between response and long-term prevention of outcomes such as hepatocellular carcinoma is not known.

Gilead Sciences, Inc.
Foster City, CA 94404

VIREAD, ATRIPLA, COMPLERA, EPCLUSA, HARVONI, HEPSERA, SOVALDI, STRIBILD, and TRUVADA are trademarks of Gilead Sciences, Inc., or its related companies. All other trademarks referenced herein are the property of their respective owners.

© 2019 Gilead Sciences, Inc. All rights reserved.

21356-GS-041

Patient Information

VIREAD® (VEER-ee-ad)
(tenofovir disoproxil fumarate)
tablets

VIREAD® (VEER-ee-ad)
(tenofovir disoproxil fumarate)
oral powder

Read this Patient Information before you start taking VIREAD and each time you get a refill. There may be new information. This information does not take the place of talking with your healthcare provider about your medical condition or treatment.

What is the most important information I should know about VIREAD?

VIREAD can cause serious side effects, including:

- Worsening of Hepatitis B virus infection (HBV). Your healthcare provider will test you for HBV and HIV before starting treatment with VIREAD. If you have HBV infection and take VIREAD your HBV may get worse (flare-up) if you stop taking VIREAD. A "flare-up" is when your HBV infection suddenly returns in a worse way than before.
  - Do not run out of VIREAD. Refill your prescription or talk to your healthcare provider before your VIREAD is all gone.
  - Do not stop taking VIREAD without first talking to your healthcare provider.
  - If you stop taking VIREAD, your healthcare provider will need to check your health often and do blood tests regularly to check your HBV infection. Tell your healthcare provider about any new or unusual symptoms you may have after you stop taking VIREAD.

For more information about side effects, see "What are the possible side effects of VIREAD?"

What is VIREAD?

VIREAD is a prescription medicine that is used to:

- treat HIV-1 infection when used with other anti-HIV-1 medicines in adults and children 2 years of age and older who weigh at least 22 pounds (10 kg). HIV is the virus that causes AIDS (Acquired Immune Deficiency Syndrome).
- treat HBV infection in adults and children 2 years of age and older who weigh at least 22 pounds (10 kg). It is not known if VIREAD is safe and effective in children under 2 years of age.

What should I tell my healthcare provider before taking VIREAD?

Before you take VIREAD, tell your healthcare provider about all of your medical conditions, including if you:

- have liver problems, including HBV infection
- have kidney problems or receive kidney dialysis treatment
- have bone problems
- have HIV infection
- are pregnant or plan to become pregnant. Tell your healthcare provider if you become pregnant during treatment with VIREAD.
  Pregnancy Registry. There is a pregnancy registry for women who take VIREAD during pregnancy. The purpose of this registry is to collect information about the health of you and your baby. Talk to your healthcare provider about how you can take part in this registry.
- are breastfeeding or plan to breastfeed. VIREAD can pass to your baby in your breast milk.
  - Do not breastfeed if you have HIV-1 because of the risk of passing HIV-1 to your baby.
  - If you take VIREAD for treatment of HBV infection, talk with your healthcare provider about the best way to feed your baby.

Tell your healthcare provider about all the medicines you take, including prescription and non-prescription medicines, vitamins, and herbal supplements.

Some medicines may interact with VIREAD. Keep a list of your medicines and show it to your healthcare provider and pharmacist when you get a new medicine.

- You can ask your healthcare provider or pharmacist for a list of medicines that interact with VIREAD.
- Do not start a new medicine without telling your healthcare provider. Your healthcare provider can tell you if it is safe to take VIREAD with other medicines.

How should I take VIREAD?

- Take VIREAD exactly as your healthcare provider tells you to take it.
- Do not change your dose or stop taking VIREAD without first talking with your healthcare provider. Stay under a healthcare provider's care when taking VIREAD.
- Take VIREAD at the same time every day.
- For adults and children 2 years of age and older who weigh at least 77 pounds (35 kg), the usual dose of VIREAD is one 300 mg tablet each day.
- For children 2 years of age and older who weigh between 37 pounds (17 kg) and 77 pounds (35 kg), your healthcare provider will prescribe the right dose of VIREAD tablets based on your child's body weight.
- Adults and children 2 years of age and older who weigh at least 22 pounds (10 kg) and who are unable to swallow VIREAD tablets whole, may take VIREAD powder. Your healthcare provider will prescribe the right dose of VIREAD powder based on your or your child's body weight.
- Tell your healthcare provider if you or your child has problems with swallowing tablets.
- If your healthcare provider prescribes VIREAD powder for you or your child, see the "Instructions for Use" that comes with your VIREAD powder for information about the right way to measure and take VIREAD powder.
- Take VIREAD tablets by mouth, with or without food.
- Do not miss a dose of VIREAD. Missing a dose lowers the amount of medicine in your blood. Refill your VIREAD prescription before you run out of medicine.
- If you take too much VIREAD, call your local poison control center or go right away to the nearest hospital emergency room.

What are the possible side effects of VIREAD?

VIREAD may cause serious side effects, including:

- See "What is the most important information I should know about VIREAD?"
- New or worse kidney problems, including kidney failure. Your healthcare provider should do blood and urine tests to check your kidneys before you start and during treatment with VIREAD. Your healthcare provider may tell you to take VIREAD less often, or to stop taking VIREAD if you get new or worse kidney problems.
- Changes in your immune system (Immune Reconstitution Syndrome) can happen when an HIV-1 infected person starts taking HIV medicines. Your immune system may get stronger and begin to fight infections that have been hidden in your body for a long time. Tell your healthcare provider right away if you start having new symptoms after starting your VIREAD for the treatment of HIV-1 infection.
- Bone problems can happen in some children or adults who take VIREAD. Bone problems include bone pain, or softening or thinning of bones, which may lead to fractures. Your healthcare provider may need to do tests to check your bones or your child's bones.
- Too much lactic acid in your blood (lactic acidosis). Too much lactic acid is a serious but rare medical emergency that can lead to death. Tell your healthcare provider right away if you get these symptoms: weakness or being more tired than usual, unusual muscle pain, being short of breath or fast breathing, stomach pain with nausea and vomiting, cold or blue hands and feet, feel dizzy or lightheaded, or a fast or abnormal heartbeat.
- Severe liver problems. In rare cases, severe liver problems can happen that can lead to death. Tell your healthcare provider right away if you get these symptoms: skin or the white part of your eyes turns yellow, dark "tea-colored" urine, light-colored stools, loss of appetite for several days or longer, nausea, or stomach-area pain.

The most common side effects in all people taking VIREAD are:

- nausea
- rash
- diarrhea
- headache

- pain
- depression
- weakness

In some people with advanced HBV-infection, other common side effects may include:

- fever
- itching
- vomiting

- stomach-area pain
- dizziness
- sleeping problems

These are not all the possible side effects of VIREAD.

Call your doctor for medical advice about side effects. You may report side effects to FDA at 1-800-FDA-1088.

How should I store VIREAD?

- Store VIREAD tablets or powder at room temperature between 68°F to 77°F (20°C to 25°C).
- Keep VIREAD in the original container.
- Keep the bottle tightly closed.
- Do not use VIREAD if the seal over the bottle opening is broken or missing.

Keep VIREAD and all medicines out of the reach of children.

General information about the safe and effective use of VIREAD.

Medicines are sometimes prescribed for purposes other than those listed in a Patient Information leaflet. Do not use VIREAD for a condition for which it was not prescribed. Do not give VIREAD to other people, even if they have the same condition you have. It may harm them. You can ask your pharmacist or healthcare provider for information about VIREAD that is written for health professionals.

A vaccine is available to protect people at risk for becoming infected with HBV. You can ask your healthcare provider for information about this vaccine.

What are the ingredients in VIREAD?

Active ingredient: tenofovir disoproxil fumarate

Inactive ingredients:

VIREAD tablets: croscarmellose sodium, lactose monohydrate, magnesium stearate, microcrystalline cellulose, and pregelatinized starch.

VIREAD powder: mannitol, hydroxypropyl cellulose, ethylcellulose, and silicon dioxide.

Tablet coating:

VIREAD tablets 300 mg: Opadry II Y-30-10671-A, which contains FD&C blue #2 aluminum lake, hypromellose 2910, lactose monohydrate, titanium dioxide, and triacetin.

VIREAD tablets 150, 200, and 250 mg: Opadry II 32K-18425, which contains hypromellose 2910, lactose monohydrate, titanium dioxide, and triacetin.

Manufactured for and distributed by: Gilead Sciences, Inc. Foster City, CA 94404
VIREAD is a trademark of Gilead Sciences, Inc., or its related companies. All other trademarks referenced herein are the property of their respective owners.
© 2019 Gilead Sciences, Inc. All rights reserved. 21356-GS-041
For more information, go to www.viread.com or call Gilead Sciences, Inc. at 1-800-GILEAD-5 (1-800-445-3235).

This Patient Information has been approved by the U.S. Food and Drug Administration.

Revised: April 2019

Instructions for Use

VIREAD® (VEER-ee-ad)
(tenofovir disoproxil fumarate)
powder
for oral use

Read the Patient Information that comes with VIREAD powder for important information about VIREAD.

Read this Instructions for Use before you give VIREAD for the first time. Be sure you understand and follow the instructions. If you have any questions, ask your healthcare provider or pharmacist.

Important information

- VIREAD powder comes in a box that has a bottle of VIREAD and a dosing scoop (see Figure A).
  Figure A
- Only use the dosing scoop to measure VIREAD powder.
- Only mix VIREAD powder with soft foods that can be swallowed without chewing. Examples of soft foods you can use are: applesauce, baby food, or yogurt.
- Do not mix VIREAD powder with liquid. The powder may float to the top even after stirring.
- Give the entire dose right away after mixing to avoid a bad taste.

How do I prepare and give a dose of VIREAD powder?

1. Wash your hands well with soap and water, and dry them.
2. Measure ¼ to ½ cup of soft food such as applesauce, baby food, or yogurt into a cup or bowl.
3. To open a new bottle of powder, press down on the bottle lid and turn to remove (see picture on the top of the bottle cap). Peel off the foil.
4. Measure the number of scoops prescribed by your healthcare provider.
  - For each full scoop prescribed:
    - Fill the dosing scoop to the top.
    - Use the flat edge of clean knife to make the powder even with the top of the scoop (see Figure B).
      Figure B
  - For ½ scoop:
    - Fill the dosing scoop up to the "½ line" on the side (see Figure C).
      Figure C
5. Sprinkle the VIREAD powder on the soft food. Stir with a spoon until well mixed. Give the entire dose right away after mixing to avoid a bad taste.
6. Close the bottle of VIREAD tightly.
7. Wash and dry the dosing scoop. Do not store the dosing scoop in the bottle.

How should I store VIREAD powder?

- Store VIREAD powder at room temperature between 68 °F to 77 °F (20 °C to 25 °C).
- Keep VIREAD powder in the original container.
- Keep the bottle tightly closed.
- Do not use VIREAD powder if the seal over the bottle opening is broken or missing.

Keep VIREAD and all medicines out of the reach of children.

This Instructions for Use has been approved by the U.S. Food and Drug Administration.

Manufactured for and distributed by: Gilead Sciences, Inc. Foster City, CA 94404

Revised: April 2019

VIREAD is a trademark of Gilead Sciences, Inc., or its related companies. All other trademarks referenced herein are the property of their respective owners.
© 2019 Gilead Sciences, Inc. All rights reserved.
21356-GS-041

PRINICPAL DISPLAY PANEL - 150 mg Tablet Bottle Label

NDC 61958-0404-1

Viread®
(tenofovir disoproxil
fumarate) tablets

150 mg

30 tablets

Rx only

PRINICPAL DISPLAY PANEL - 200 mg Tablet Bottle Label

NDC 61958-0405-1

Viread®
(tenofovir disoproxil
fumarate) tablets

200 mg

30 tablets

Rx only

PRINICPAL DISPLAY PANEL - 250 mg Tablet Bottle Label

NDC 61958-0406-1

Viread®
(tenofovir disoproxil
fumarate) tablets

250 mg

30 tablets

Rx only

PRINICPAL DISPLAY PANEL - 300 mg Tablet Bottle Label

NDC 61958-0401-1

Viread®
(tenofovir disoproxil
fumarate) tablets

300 mg

30 tablets

Rx only

PRINICPAL DISPLAY PANEL - 40 mg/Scoop Bottle Label

NDC 61958-0403-1

Viread®
(tenofovir disoproxil
fumarate) Oral Powder
40 mg/scoop

60 g per bottle

Rx only